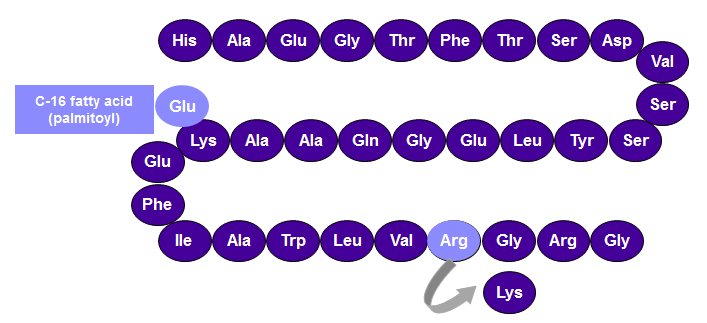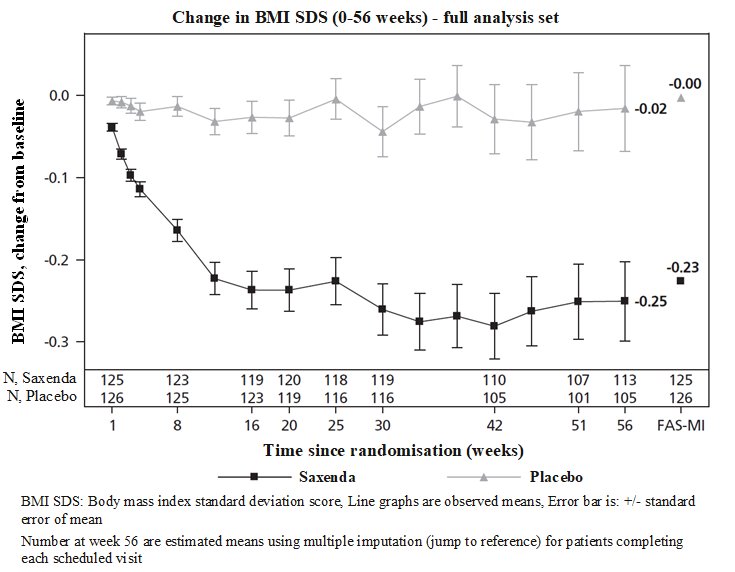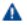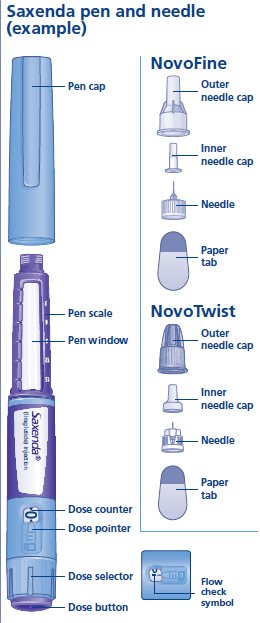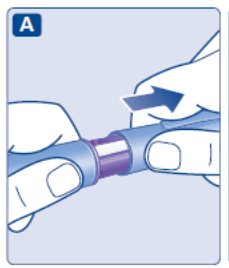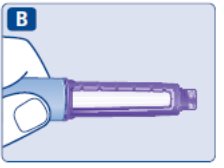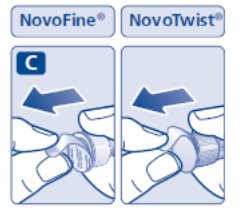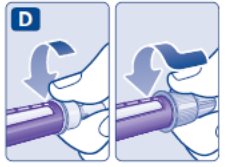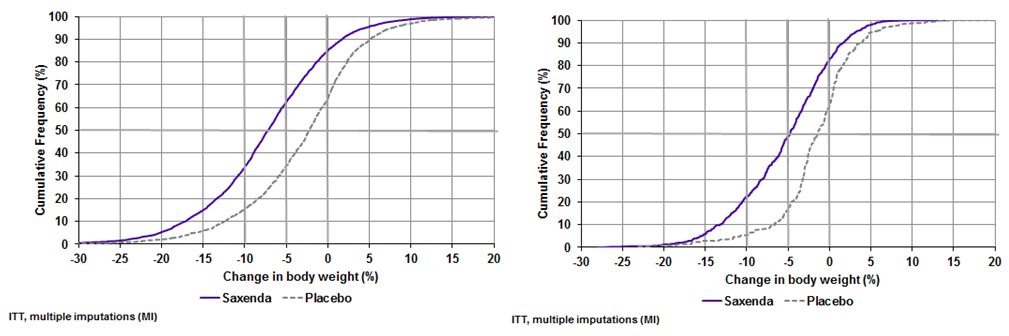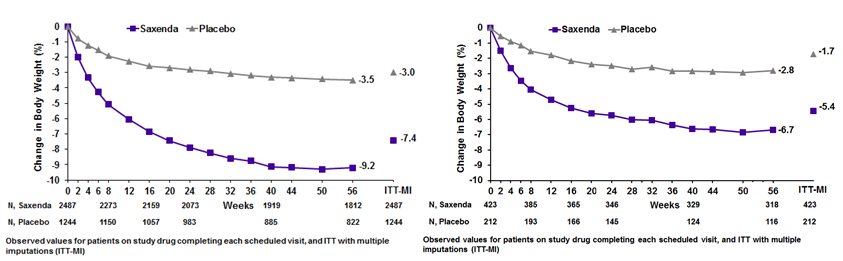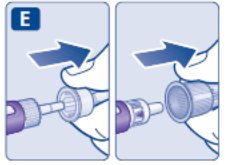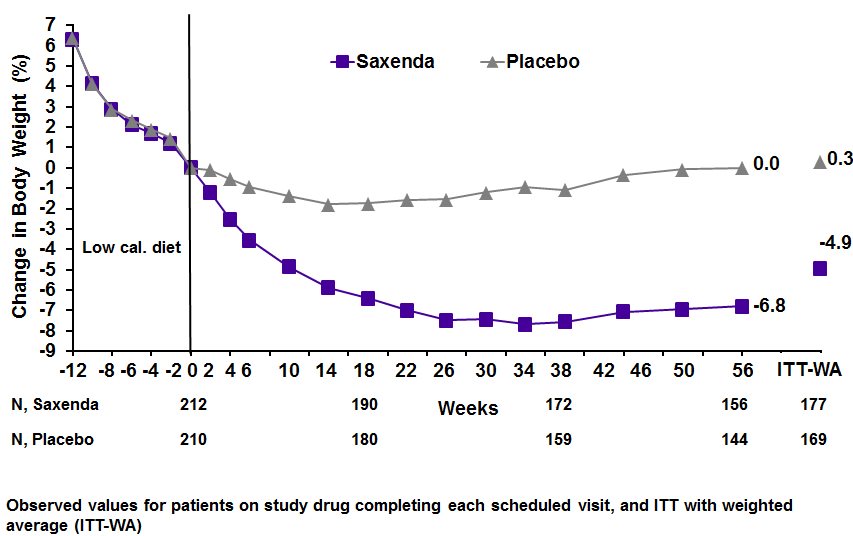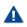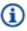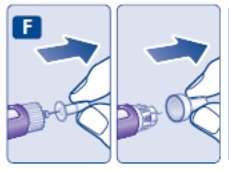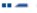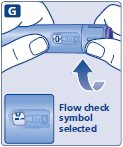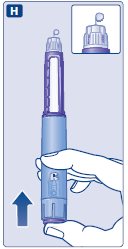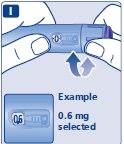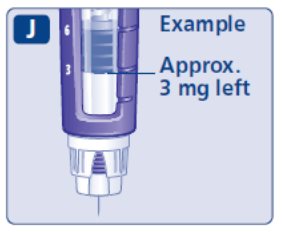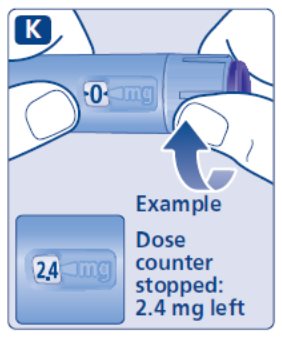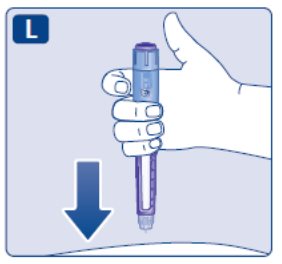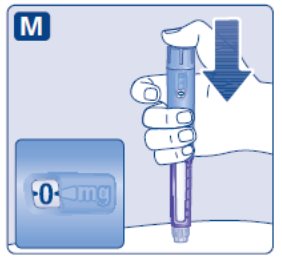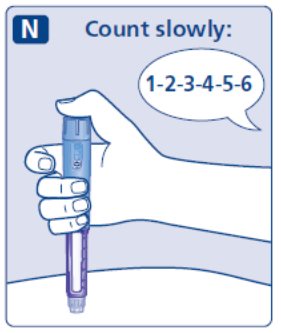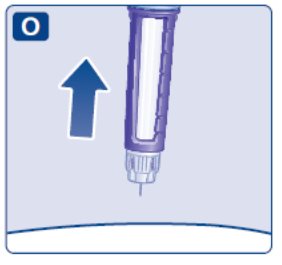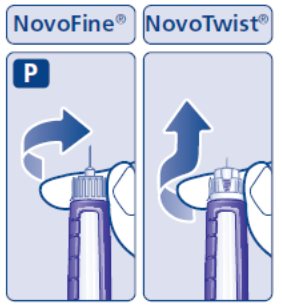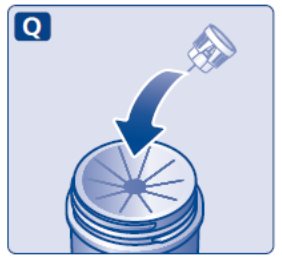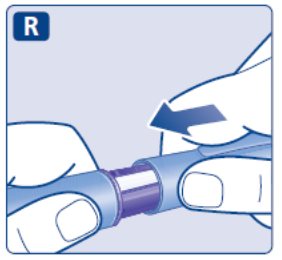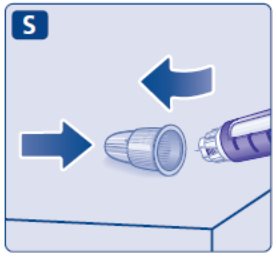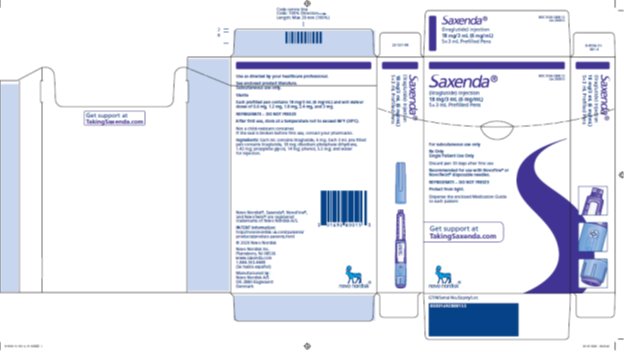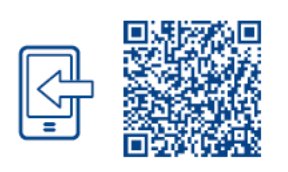 DRUG LABEL: Saxenda
NDC: 0169-2800 | Form: INJECTION, SOLUTION
Manufacturer: Novo Nordisk
Category: prescription | Type: HUMAN PRESCRIPTION DRUG LABEL
Date: 20251014

ACTIVE INGREDIENTS: LIRAGLUTIDE 6 mg/1 mL
INACTIVE INGREDIENTS: PROPYLENE GLYCOL 14 mg/1 mL; PHENOL 5.5 mg/1 mL; WATER; SODIUM PHOSPHATE, DIBASIC, DIHYDRATE 1.42 mg/1 mL

HIGHLIGHTS OF PRESCRIBING INFORMATION

These highlights do not include all the information needed to use SAXENDA® safely and effectively. See full prescribing information for SAXENDA.
SAXENDA (liraglutide) injection, for subcutaneous use
Initial U.S. Approval: 2010

RECENT MAJOR CHANGES

Indications and Usage (1).………………………………….……….05/2025

Dosage and Administration, Patient Selection (2.1)..…..(Removed) 05/2025

Contraindications, Pregnancy (4).………………………(Removed) 05/2025

Warnings and Precautions,
  Severe Gastrointestinal Adverse Reactions (5.7)………..………10/2025
Pulmonary Aspiration During General Anesthesia
  or Deep Sedation (5.10)……………………………………….....11/2024

WARNING: RISK OF THYROID C-CELL TUMORS

See full prescribing information for complete boxed warning.

- Liraglutide causes thyroid C-cell tumors at clinically relevant exposures in both genders of rats and mice. It is unknown whether SAXENDA causes thyroid C-cell tumors, including medullary thyroid carcinoma (MTC), in humans, as the human relevance of liraglutide-induced rodent thyroid C-cell tumors has not been determined (5.1).
- SAXENDA is contraindicated in patients with a personal or family history of MTC or in patients with Multiple Endocrine Neoplasia syndrome type 2 (MEN 2). Counsel patients regarding the potential risk of MTC and the symptoms of thyroid tumors (4, 5.1, 13.1).

1 INDICATIONS AND USAGE

SAXENDA is a glucagon like peptide 1 (GLP-1) receptor agonist indicated in combination with a reduced calorie diet and increased physical activity to reduce excess body weight and maintain weight reduction long term in:

- Adults and pediatric patients aged 12 years and older with body weight greater than 60 kg and obesity. (1)
- Adults with overweight in the presence of at least one weight-related comorbid condition. (1)

Limitations of Use:

  - Coadministration with other liraglutide-containing products or with any other GLP-1 receptor agonist is not recommended. (1)
  - The safety and effectiveness of SAXENDA in pediatric patients with type 2 diabetes have not been established. (1)

2 DOSAGE AND ADMINISTRATION

- Inject SAXENDA subcutaneously in the abdomen, thigh, or upper arm once daily at any time of day, without regard to the timing of meals. (2.1)
- The recommended dose of SAXENDA is 3 mg daily. (2.2)
- Initiate at 0.6 mg per day for one week. In weekly intervals, increase the dose until a dose of 3 mg is reached. (2.2)
- If pediatric patients do not tolerate an increased dose during dose escalation, the dose may also be lowered to the previous level. Dose escalation for pediatric patients may take up to 8 weeks. (2.2)
- Pediatric patients who do not tolerate 3 mg daily may have their dose reduced to 2.4 mg daily. (2.2)
- Adult patients with type 2 diabetes should monitor blood glucose prior to starting SAXENDA and during SAXENDA treatment. (2.2)

3 DOSAGE FORMS AND STRENGTHS

Injection: 6 mg/mL solution in a 3 mL prefilled, single-patient-use pen that delivers doses of 0.6 mg, 1.2 mg, 1.8 mg, 2.4 mg or 3 mg. (3)

4 CONTRAINDICATIONS

- Personal or family history of medullary thyroid carcinoma or Multiple Endocrine Neoplasia syndrome type 2. (4)
- Hypersensitivity to liraglutide or any excipients in SAXENDA. (4)

5 WARNINGS AND PRECAUTIONS

- Acute Pancreatitis: Has been observed in patients treated with GLP-1 receptor agonists, including SAXENDA. Discontinue if pancreatitis is suspected. (5.2)
- Acute Gallbladder Disease: If cholelithiasis or cholecystitis are suspected, gallbladder studies are indicated. (5.3)
- Hypoglycemia: Can occur in adults when SAXENDA is used with an insulin secretagogue (e.g. a sulfonylurea) or insulin. The risk may be lowered by a reduction in the dose of concomitantly administered insulin secretagogues or insulin. In the pediatric clinical trial, patients did not have type 2 diabetes. Hypoglycemia occurred in SAXENDA-treated pediatric patients. Inform all patients of the risk of hypoglycemia and educate them on the signs and symptoms of hypoglycemia. (5.4)
- Heart Rate Increase: Monitor heart rate at regular intervals. (5.5)
- Acute Kidney Injury Due to Volume Depletion: Monitor renal function in patients reporting adverse reactions that could lead to volume depletion. (5.6)
- Severe Gastrointestinal Adverse Reactions: Use has been associated with gastrointestinal adverse reactions, sometimes severe. SAXENDA is not recommended in patients with severe gastroparesis. (5.7)
- Hypersensitivity Reactions: Postmarketing reports of serious hypersensitivity reactions (e.g., anaphylactic reactions and angioedema). Discontinue SAXENDA and other suspect medications and promptly seek medical advice. (5.8)
- Suicidal Behavior and Ideation: Monitor for depression or suicidal thoughts. Discontinue SAXENDA if symptoms develop. (5.9)
- Pulmonary Aspiration During General Anesthesia or Deep Sedation: Has been reported in patients receiving GLP-1 receptor agonists undergoing elective surgeries or procedures. Instruct patients to inform healthcare providers of any planned surgeries or procedures. (5.10)

6 ADVERSE REACTIONS

Most common adverse reactions, reported in greater than or equal to 5% are: nausea, diarrhea, constipation, vomiting, injection site reactions, headache, hypoglycemia, dyspepsia, fatigue, dizziness, abdominal pain, increased lipase, upper abdominal pain, pyrexia, and gastroenteritis. (6.1)

To report SUSPECTED ADVERSE REACTIONS, contact Novo Nordisk Inc. at 1-844-363-4448 or FDA at 1-800-FDA-1088 or www.fda.gov/medwatch.

7 DRUG INTERACTIONS

SAXENDA delays gastric emptying. May impact absorption of concomitantly administered oral medications. Use with caution. (7)

8 USE IN SPECIFIC POPULATIONS

Pregnancy: May cause fetal harm. When pregnancy is recognized, discontinue SAXENDA. (8.1)

FULL PRESCRIBING INFORMATION

WARNING: RISK OF THYROID C-CELL TUMORS

- Liraglutide causes dose-dependent and treatment-duration-dependent thyroid C-cell tumors at clinically relevant exposures in both genders of rats and mice. It is unknown whether SAXENDA causes thyroid C-cell tumors, including medullary thyroid carcinoma (MTC), in humans, as the human relevance of liraglutide-induced rodent thyroid C-cell tumors has not been determined [see Warnings and Precautions (5.1), Nonclinical Toxicology (13.1)].
- SAXENDA is contraindicated in patients with a personal or family history of MTC and in patients with Multiple Endocrine Neoplasia syndrome type 2 (MEN 2). Counsel patients regarding the potential risk of MTC with use of SAXENDA and inform them of symptoms of thyroid tumors (e.g., a mass in the neck, dysphagia, dyspnea, persistent hoarseness). Routine monitoring of serum calcitonin or using thyroid ultrasound is of uncertain value for early detection of MTC in patients treated with SAXENDA [see Contraindications (4), Warnings and Precautions (5.1)].

1 INDICATIONS AND USAGE

SAXENDA is indicated in combination with a reduced calorie diet and increased physical activity to reduce excess body weight and maintain weight reduction long term in:

- Adults and pediatric patients aged 12 years and older with body weight greater than 60 kg and obesity.
- Adults with overweight in the presence of at least one weight-related comorbid condition.

Limitations of Use

- SAXENDA contains liraglutide. Coadministration with other liraglutide-containing products or with any other glucagon-like peptide-1 (GLP-1) receptor agonist is not recommended.
- The safety and effectiveness of SAXENDA in pediatric patients with type 2 diabetes have not been established.

2 DOSAGE AND ADMINISTRATION

2.1 Important Administration Instructions

- Prior to initiation of SAXENDA, train patients on proper injection technique. Refer to the accompanying Instructions for Use for complete administration instructions with illustrations.
- Inspect SAXENDA visually prior to each injection. Only use if solution is clear, colorless, and contains no particles.
- Administer SAXENDA in combination with a reduced-calorie diet and increased physical activity.
- Inject SAXENDA subcutaneously once daily at any time of day, without regard to the timing of meals.
- Inject SAXENDA subcutaneously in the abdomen, thigh, or upper arm. No dosage adjustment is needed if changing the injection site and/or timing.
- Rotate injection sites within the same region in order to reduce the risk of cutaneous amyloidosis [see Adverse Reactions (6.2)].
- If a dose is missed, resume the once-daily regimen as prescribed with the next scheduled dose. Do not administer an extra dose or increase the dose to make up for the missed dose.
- If more than 3 days have elapsed since the last SAXENDA dosage, reinitiate SAXENDA at 0.6 mg daily and follow the dosage escalation schedule in Table 1, to reduce the risk of gastrointestinal adverse reactions associated with reinitiation of treatment.

2.2 Dosage in Adults and Pediatric Patients Aged 12 Years and Older

- Initiate SAXENDA with a dose of 0.6 mg daily for one week. Then follow the dosage escalation schedule in Table 1 to reduce the risk of gastrointestinal adverse reactions [see Warnings and Precautions (5.7), Adverse Reactions (6.1)].

Table 1. Dosage Escalation Schedule

Week | Daily Dose
1 | 0.6 mg
2 | 1.2 mg
3 | 1.8 mg
4 | 2.4 mg
5 and onward | 3 mg

Adult Patients
2. For adults, the recommended dosage of SAXENDA is 3 mg daily, lower dosages are for titration only.
3. Discontinue SAXENDA if the patient cannot tolerate the 3 mg dosage.
4. If patients do not tolerate an increased dose during dosage escalation, consider delaying dosage escalation for approximately one additional week.
5. Evaluate the change in body weight 16 weeks after initiating SAXENDA and discontinue SAXENDA if the patient has not lost at least 4% of baseline body weight, since it is unlikely that the patient will achieve and sustain clinically meaningful weight loss with continued treatment.
6. In adult patients with type 2 diabetes, monitor blood glucose prior to starting SAXENDA and during SAXENDA treatment.

Pediatric Patients

- For pediatric patients, the recommended maintenance dosage of SAXENDA is 3 mg daily. Pediatric patients who do not tolerate 3 mg daily may have their maintenance dose reduced to 2.4 mg daily. Discontinue SAXENDA if the patient cannot tolerate the 2.4 mg dose.
- If pediatric patients do not tolerate an increased dose during dosage escalation, the dose may also be lowered to the previous level. Dosage escalation for pediatric patients may take up to 8 weeks.
- Evaluate the change in BMI after 12 weeks on the maintenance dose and discontinue SAXENDA if the patient has not had a reduction in BMI of at least 1% from baseline, since it is unlikely that the patient will achieve and sustain clinically meaningful weight loss with continued treatment.

3 DOSAGE FORMS AND STRENGTHS

Injection: 6 mg/mL clear, colorless solution in a 3 mL prefilled, single-patient-use pen that delivers doses of 0.6 mg, 1.2 mg, 1.8 mg, 2.4 mg, or 3 mg.

4 CONTRAINDICATIONS

SAXENDA is contraindicated in:

- Patients with a personal or family history of medullary thyroid carcinoma (MTC) or patients with Multiple Endocrine Neoplasia syndrome type 2 (MEN 2) [see Warnings and Precautions (5.1)].
- Patients with a serious hypersensitivity reaction to liraglutide or to any of the excipients in SAXENDA. Serious hypersensitivity reactions including anaphylactic reactions and angioedema have been reported with SAXENDA [see Warnings and Precautions (5.8)].

5 WARNINGS AND PRECAUTIONS

5.1 Risk of Thyroid C-cell Tumors

Liraglutide causes dose-dependent and treatment-duration-dependent thyroid C-cell tumors (adenomas and/or carcinomas) at clinically relevant exposures in both genders of rats and mice [see Nonclinical Toxicology (13.1)]. Malignant thyroid C-cell carcinomas were detected in rats and mice. It is unknown whether SAXENDA will cause thyroid C-cell tumors, including medullary thyroid carcinoma (MTC), in humans, as the human relevance of liraglutide-induced rodent thyroid C-cell tumors has not been determined.

Cases of MTC in patients treated with liraglutide have been reported in the postmarketing period; the data in these reports are insufficient to establish or exclude a causal relationship between MTC and liraglutide use in humans.

SAXENDA is contraindicated in patients with a personal or family history of MTC or in patients with MEN 2. Counsel patients regarding the potential risk for MTC with the use of SAXENDA and inform them of symptoms of thyroid tumors (e.g., a mass in the neck, dysphagia, dyspnea, persistent hoarseness).

Routine monitoring of serum calcitonin or using thyroid ultrasound is of uncertain value for early detection of MTC in patients treated with SAXENDA. Such monitoring may increase the risk of unnecessary procedures, due to low test specificity for serum calcitonin and a high background incidence of thyroid disease. Significantly elevated serum calcitonin may indicate MTC, and patients with MTC usually have calcitonin values greater than 50 ng/L. If serum calcitonin is measured and found to be elevated, the patient should be further evaluated. Patients with thyroid nodules noted on physical examination or neck imaging should also be further evaluated.

5.2 Acute Pancreatitis

Acute pancreatitis, including fatal and non-fatal hemorrhagic or necrotizing pancreatitis, has been observed in patients treated with GLP-1 receptor agonists, including liraglutide [see Adverse Reactions (6)].

After initiation of SAXENDA, observe patients carefully for signs and symptoms of acute pancreatitis which may include persistent or severe abdominal pain (sometimes radiating to the back) and which may or may not be accompanied by nausea or vomiting. If pancreatitis is suspected, discontinue SAXENDA and initiate appropriate management.

5.3 Acute Gallbladder Disease

In SAXENDA clinical trials in adults, 2.2% of SAXENDA-treated patients reported adverse events of cholelithiasis versus 0.8% of placebo-treated patients. The incidence of cholecystitis was 0.8% in SAXENDA-treated patients versus 0.4% in placebo-treated patients. The majority of SAXENDA-treated patients with adverse events of cholelithiasis and cholecystitis required cholecystectomy. Substantial or rapid weight loss can increase the risk of cholelithiasis; however, the incidence of acute gallbladder disease was greater in SAXENDA-treated patients than in placebo-treated patients even after accounting for the degree of weight loss. If cholelithiasis is suspected, gallbladder studies and appropriate clinical follow-up are indicated.

5.4 Hypoglycemia

Adult patients with type 2 diabetes mellitus on an insulin secretagogue (e.g., sulfonylurea) or insulin may have an increased risk of hypoglycemia with use of SAXENDA, including severe hypoglycemia. In patients with type 2 diabetes, monitor blood glucose prior to starting SAXENDA and during SAXENDA treatment [see Dosage and Administration (2), Adverse Reactions (6.1)].

The risk of hypoglycemia may be lowered by a reduction in the dose of sulfonylurea (or other concomitantly administered insulin secretagogues) or insulin. Inform patients using these concomitant medications of the risk of hypoglycemia and educate them on the signs and symptoms of hypoglycemia.

In the pediatric clinical trial, patients did not have type 2 diabetes but were provided with blood glucose meters. Clinically significant hypoglycemia, defined as blood glucose <54 mg/dL, occurred in 1.6% of the SAXENDA- treated patients compared to 0.8% of placebo-treated patients [see Adverse Reactions (6.1)]. Inform all pediatric patients of the risk of hypoglycemia and educate them on the signs and symptoms of hypoglycemia.

5.5 Heart Rate Increase

Mean increases in resting heart rate of 2 to 3 beats per minute (bpm) were observed with routine clinical monitoring in SAXENDA-treated adult patients compared to placebo in clinical trials. More patients treated with SAXENDA, compared with placebo, had changes from baseline at two consecutive visits of more than 10 bpm (34% versus 19%, respectively) and 20 bpm (5% versus 2%, respectively). At least one resting heart rate exceeding 100 bpm was recorded for 6% of SAXENDA-treated patients compared with 4% of placebo-treated patients, with this occurring at two consecutive study visits for 0.9% and 0.3%, respectively. Tachycardia was reported as an adverse reaction in 0.6% of SAXENDA-treated patients and in 0.1% of placebo-treated patients.

In a clinical pharmacology trial that monitored heart rate continuously for 24 hours, SAXENDA treatment was associated with a heart rate that was 4 to 9 bpm higher than that observed with placebo.

In a pediatric clinical trial, mean increases from baseline in resting heart rate of 3 to 7 bpm were observed with SAXENDA treatment.

Heart rate should be monitored at regular intervals consistent with usual clinical practice. Patients should inform health care providers of palpitations or feelings of a racing heartbeat while at rest during SAXENDA treatment. For patients who experience a sustained increase in resting heart rate while taking SAXENDA, SAXENDA should be discontinued.

5.6 Acute Kidney Injury Due to Volume Depletion

There have been postmarketing reports of acute kidney injury, in some cases requiring hemodialysis, in patients treated with liraglutide [see Adverse Reactions (6.2)]. The majority of the reported events occurred in patients who had experienced gastrointestinal reactions leading to dehydration such as nausea, vomiting, or diarrhea [see Adverse Reactions (6.1)]. Monitor renal function in patients reporting adverse reactions to SAXENDA that could lead to volume depletion, especially during dosage initiation and escalation [see Use in Specific Populations (8.6)].

5.7 Severe Gastrointestinal Adverse Reactions

Use of GLP-1 receptor agonists, including liraglutide, has been associated with gastrointestinal adverse reactions, sometimes severe [see Adverse Reactions (6)]. In SAXENDA clinical trials, severe gastrointestinal adverse reactions were reported more frequently among patients receiving SAXENDA (4.8%) than placebo (1.4%). Severe gastrointestinal adverse reactions have also been reported postmarketing with GLP-1 receptor agonists. SAXENDA is not recommended in patients with severe gastroparesis.

5.8 Hypersensitivity Reactions

There have been reports of serious hypersensitivity reactions (e.g., anaphylactic reactions and angioedema) in patients treated with SAXENDA [see Contraindications (4), Adverse Reactions (6.1, 6.2)]. If a hypersensitivity reaction occurs, the patient should discontinue SAXENDA and other suspect medications and promptly seek medical advice.

Anaphylaxis and angioedema have been reported with other GLP-1 receptor agonists. Use caution in a patient with a history of anaphylaxis or angioedema with another GLP-1 receptor agonist because it is unknown whether such patients will be predisposed to these reactions with SAXENDA.

5.9 Suicidal Behavior and Ideation

In SAXENDA adult clinical trials, 9 (0.3%) of 3384 SAXENDA-treated patients and 2 (0.1%) of the 1941 placebo-treated patients reported suicidal ideation; one of these SAXENDA-treated patients attempted suicide.

In a SAXENDA pediatric clinical trial, 1 (0.8%) of the 125 SAXENDA-treated patients died by suicide. There was insufficient information to establish a causal relationship to SAXENDA.

Patients treated with SAXENDA should be monitored for the emergence or worsening of depression, suicidal thoughts or behavior, and/or any unusual changes in mood or behavior. Discontinue SAXENDA in patients who experience suicidal thoughts or behaviors. Avoid SAXENDA in patients with a history of suicidal attempts or active suicidal ideation.

5.10 Pulmonary Aspiration During General Anesthesia or Deep Sedation

SAXENDA delays gastric emptying [see Clinical Pharmacology (12.2)]. There have been rare postmarketing reports of pulmonary aspiration in patients receiving GLP-1 receptor agonists undergoing elective surgeries or procedures requiring general anesthesia or deep sedation who had residual gastric contents despite reported adherence to preoperative fasting recommendations.

Available data are insufficient to inform recommendations to mitigate the risk of pulmonary aspiration during general anesthesia or deep sedation in patients taking SAXENDA, including whether modifying preoperative fasting recommendations or temporarily discontinuing SAXENDA could reduce the incidence of retained gastric contents. Instruct patients to inform healthcare providers prior to any planned surgeries or procedures if they are taking SAXENDA.

6 ADVERSE REACTIONS

The following serious adverse reactions are described below or elsewhere in the prescribing information:

- Risk of Thyroid C-Cell Tumors [see Warnings and Precautions (5.1)]
- Acute Pancreatitis [see Warnings and Precautions (5.2)]
- Acute Gallbladder Disease [see Warnings and Precautions (5.3)]
- Risk for Hypoglycemia with Concomitant Use of Anti-Diabetic Therapy [see Warnings and Precautions (5.4)]
- Heart Rate Increase [see Warnings and Precautions (5.5)]
- Acute Kidney Injury Due to Volume Depletion [see Warnings and Precautions (5.6)]
- Severe Gastrointestinal Adverse Reactions [see Warnings and Precautions (5.7)]
- Hypersensitivity Reactions [see Warnings and Precautions (5.8)]
- Suicidal Behavior and Ideation [see Warnings and Precautions (5.9)]
- Pulmonary Aspiration During General Anesthesia or Deep Sedation [see Warnings and Precautions (5.10)]

6.1 Clinical Trials Experience

Because clinical trials are conducted under widely varying conditions, adverse reaction rates observed in the clinical trials of a drug cannot be directly compared to rates in the clinical studies of another drug and may not reflect the rates observed in practice.

SAXENDA was evaluated for safety in 5 double-blind, placebo controlled trials that included 3384 overweight or obese adult patients treated with SAXENDA for a treatment period up to 56 weeks (3 trials), 52 weeks (1 trial), and 32 weeks (1 trial) and one trial of 56 weeks in 125 pediatric patients with obesity aged 12 years and older [see Clinical Studies (14.1, 14.2)]. All patients received study drug in addition to a reduced-calorie diet and increased physical activity counseling. In the adult trials, patients received SAXENDA for a mean treatment duration of 46 weeks (median, 56 weeks). Baseline characteristics included a mean age of 47 years, 71% female, 85% white, 39% with hypertension, 15% with type 2 diabetes, 34% with dyslipidemia, 29% with a BMI greater than 40 kg/m^2, and 9% with cardiovascular disease. In one of the 56-week trials, a subset of patients (with abnormal glucose measurements at randomization) [see Clinical Studies (14.1)] were enrolled for a placebo-controlled 160-week period instead, followed by a 12-week off-treatment follow-up. For those participating in this 160-week period, patients received SAXENDA for a mean treatment duration of 110 weeks (median, 159 weeks). For all trials, dosing was initiated and increased weekly to reach the 3 mg dose.

In adult clinical trials, 9.8% of patients treated with SAXENDA and 4.3% of patients treated with placebo prematurely discontinued treatment as a result of adverse reactions. The most common adverse reactions leading to discontinuation were nausea (2.9% versus 0.2% for SAXENDA and placebo, respectively), vomiting (1.7% versus less than 0.1%), and diarrhea (1.4% versus 0%).

Adverse reactions reported in greater than or equal to 2% of SAXENDA-treated adult patients and more frequently than in placebo-treated patients are shown in Table 2. Adverse reactions reported in greater than or equal to 3% of SAXENDA-treated pediatric patients and more frequently than in placebo-treated patients are shown in Table 3.

Table 2. Adverse Reactions Occurring in ≥2% of SAXENDA-treated Adult Patients and More Frequently than Placebo

 | Placebo; N=1941; % | SAXENDA; N=3384; %
Nausea | 13.8 | 39.3
Diarrhea | 9.9 | 20.9
Constipation | 8.5 | 19.4
Vomiting | 3.9 | 15.7
Injection Site Reaction^1 | 10.5 | 13.9
Headache | 12.6 | 13.6
Hypoglycemia in T2DM^2 | 6.6 | 12.6
Dyspepsia | 2.7 | 9.6
Fatigue | 4.6 | 7.5
Dizziness | 5 | 6.9
Abdominal Pain | 3.1 | 5.4
Increased Lipase | 2.2 | 5.3
Upper Abdominal Pain | 2.7 | 5.1
Gastroenteritis | 3.2 | 4.7
Gastroesophageal Reflux Disease | 1.7 | 4.7
Abdominal Distension | 3 | 4.5
Eructation | 0.2 | 4.5
Urinary Tract Infection | 3.1 | 4.3
Flatulence | 2.5 | 4
Viral Gastroenteritis | 1.6 | 2.8
Insomnia | 1.7 | 2.4
Dry Mouth | 1 | 2.3
Asthenia | 0.8 | 2.1
Anxiety | 1.6 | 2

^1 The most common reactions, each reported by 1% to 2.5% of SAXENDA-treated patients and more commonly than by placebo-treated patients, included erythema, pruritus, and rash at the injection site.

^2 Defined as blood glucose <54 mg/dL with or without symptoms of hypoglycemia in patients with type 2 diabetes not on concomitant insulin (Study 2, SAXENDA N=423, Placebo N=212). See text below for further information regarding hypoglycemia in patients with and without type 2 diabetes. T2DM = type 2 diabetes mellitus.

Table 3. Adverse Reactions Occurring in ≥3% of SAXENDA-treated Pediatric Patients and More Frequently than Placebo in a 56 Week Clinical Trial

 | Placebo; N=126; % | SAXENDA; N=125; %
Nausea | 14.3 | 42.4
Vomiting | 4 | 34.4
Diarrhea | 14.3 | 22.4
Hypoglycemia^1 | 4 | 15.2
Gastroenteritis | 4.8 | 12.8
Dizziness | 3.2 | 10.4
Pyrexia | 7.1 | 8
Abdominal discomfort | 0.8 | 4.8
Constipation | 2.4 | 4.8
Dyslipidemia | 3.2 | 4.8
Fatigue | 3.2 | 4.8
Cough | 3.2 | 4
Depression | 2.4 | 4
Dyspepsia | 2.4 | 4
Pain in extremity | 2.4 | 4
Injection site pain | 3.2 | 3.2
Flatulence | 0 | 3.2
Increased Blood Creatine Kinase | 2.4 | 3.2
Increased Lipase | 0.8 | 3.2
Rash | 0 | 3.2

^1 Defined as blood glucose <70 mg/dL with symptoms of hypoglycemia. Pediatric patients did not have type 2 diabetes mellitus. See text below for more detailed hypoglycemia information.

Hypoglycemia

Adult Patients with Type 2 Diabetes

In a clinical trial in adult patients with type 2 diabetes mellitus and overweight (excess weight) or obesity, severe hypoglycemia (defined as requiring the assistance of another person) occurred in 3 (0.7%) of 422 SAXENDA-treated patients (all taking a sulfonylurea) and in none of the 212 placebo-treated patients. In this trial, among patients taking a sulfonylurea, hypoglycemia defined as a plasma glucose less than 54 mg/dL with or without symptoms occurred in 31 (28.2%) of 110 SAXENDA-treated patients and 7 (12.7%) of 55 placebo-treated patients. The doses of sulfonylureas were reduced by 50% at the beginning of the trial per protocol. Among patients not taking a sulfonylurea, blood glucose less than 54 mg/dL with or without symptoms occurred in 22 (7.1%) of 312 SAXENDA-treated patients and 7 (4.5%) of 157 placebo-treated patients.

In a SAXENDA clinical trial in adult patients with overweight (excess weight) or obesity with type 2 diabetes mellitus treated with basal insulin and SAXENDA in combination with a reduced-calorie diet and increased physical activity and up to 2 oral anti-diabetes medications, severe hypoglycemia was reported by 3 (1.5%) of 195 SAXENDA-treated patients and 2 (1%) of 197 placebo-treated patients. No meaningful difference in hypoglycemia, defined as blood glucose less than 54 mg/dL with or without symptoms, was reported between groups.

Adult Patients without Type 2 Diabetes

In SAXENDA clinical trials in adult patients without type 2 diabetes mellitus, there was no systematic capturing or reporting of hypoglycemia; patients were not provided with blood glucose meters or hypoglycemia diaries. Spontaneously reported symptomatic episodes of unconfirmed hypoglycemia were reported by 46 (1.6%) of 2962 SAXENDA-treated patients and 19 (1.1%) of 1729 placebo-treated patients. Fasting plasma glucose values obtained at routine clinic visits less than 54 mg/dL, irrespective of hypoglycemic symptoms, occurred in 2 (0.1%) SAXENDA-treated patients and 1 (0.1%) placebo-treated patients.

Pediatric Patients without Type 2 Diabetes

In a 56-week placebo-controlled clinical trial of pediatric patients without type 2 diabetes mellitus in which blood glucose meters were provided, 19 (15.2%) of SAXENDA-treated patients had hypoglycemia with a blood glucose less than 70 mg/dL with symptoms as compared to 5 (4%) of placebo-treated patients. Four (4) events of hypoglycemia defined as a plasma glucose less than 54 mg/dL occurred in 2 (1.6%) of 125 SAXENDA-treated patients and 1 event occurred in 1 (0.8%) of 126 placebo-treated patients. No severe hypoglycemic episodes, defined as requiring assistance of another person to actively administer carbohydrate, glucagon, or other resuscitative actions, occurred in the SAXENDA treatment group.

Acute Pancreatitis

In SAXENDA clinical trials in adults, acute pancreatitis was confirmed by adjudication in 9 (0.3%) of 3291 SAXENDA-treated patients and 2 (0.1%) of 1843 placebo-treated patients. In addition, there were 2 cases of acute pancreatitis in SAXENDA-treated patients who prematurely withdrew from these clinical trials, occurring 74 and 124 days after the last dose. There were 2 additional cases in SAXENDA-treated patients, 1 during an off-treatment follow-up period within 2 weeks of discontinuing SAXENDA, and 1 that occurred in a patient who completed treatment and was off-treatment for 106 days.

In a SAXENDA pediatric clinical trial, pancreatitis was not independently adjudicated. Pancreatitis was reported in 1 (0.8%) SAXENDA-treated patient and resulted in treatment discontinuation.

Gastrointestinal Adverse Reactions

In the adult clinical trials, approximately 68% of SAXENDA-treated patients and 39% of placebo-treated patients reported gastrointestinal disorders; the most frequently reported was nausea (39% and 14% of patients treated with SAXENDA and placebo, respectively). Severe gastrointestinal adverse reactions were reported more frequently among patients receiving SAXENDA (4.8%) than placebo (1.4 %). There have been reports of gastrointestinal adverse reactions, such as nausea, vomiting, and diarrhea, associated with volume depletion and renal impairment. Most episodes of gastrointestinal events were mild or moderate and did not lead to discontinuation of therapy (6.2% with SAXENDA versus 0.8% with placebo discontinued treatment as a result of gastrointestinal adverse reactions). The percentage of patients reporting nausea declined as treatment continued. Other common adverse reactions that occurred at a higher incidence among SAXENDA-treated patients included diarrhea, constipation, vomiting, dyspepsia, abdominal pain, dry mouth, gastritis, gastroesophageal reflux disease, flatulence, eructation and abdominal distension. There have been reports of gastrointestinal adverse reactions, such as nausea, vomiting, and diarrhea, associated with volume depletion and renal impairment.

In a pediatric clinical trial, 8% of patients treated with SAXENDA versus no patients who received placebo discontinued treatment as a result of gastrointestinal adverse reactions. Most adverse reactions leading to discontinuation were due to vomiting and nausea (4.8% and 3.2% of SAXENDA-treated patients, respectively).

Cardiovascular Safety

Cardiovascular safety was assessed (LEADER, NCT01179048) in 9,340 patients with inadequately controlled type 2 diabetes and cardiovascular disease randomized to liraglutide 1.8 mg or placebo in addition to standard of care treatments for type 2 diabetes for a median duration of 3.5 years. The primary endpoint was the time from randomization to first occurrence of a major adverse cardiovascular event (MACE) defined as:
cardiovascular death, non-fatal myocardial infarction, or non-fatal stroke. No increased risk for MACE was observed with liraglutide 1.8 mg. The total number of primary component MACE endpoints was 1,302 [608 (13.0%) with liraglutide 1.8 mg and 694 (14.9%) with placebo]. Liraglutide 1.8 mg (Victoza) is used in the treatment of type 2 diabetes mellitus in adults. The efficacy of liraglutide at doses below 3 mg daily has not been established for weight reduction.

Asthenia, Fatigue, Malaise, Dysgeusia and Dizziness

Events of asthenia, fatigue, malaise, dysgeusia and dizziness were mainly reported within the first 12 weeks of treatment with SAXENDA and were often co-reported with gastrointestinal events such as nausea, vomiting, and diarrhea.

Immunogenicity

The detection of antibody formation is highly dependent on the sensitivity and specificity of the assay. Additionally, the observed incidence of antibody (including neutralizing antibody) positivity in an assay may be influenced by several factors including assay methodology, sample handling, timing of sample collection, concomitant medications, and underlying disease. For these reasons, the incidence of antibodies to SAXENDA cannot be directly compared with the incidence of antibodies of other products.

Patients treated with SAXENDA may develop anti-liraglutide antibodies. Anti-liraglutide antibodies were detected in 42 (2.8%) of 1505 SAXENDA-treated adult patients with a post-baseline assessment. Antibodies that had a neutralizing effect on liraglutide in an in vitro assay occurred in 18 (1.2%) of 1505 SAXENDA-treated patients. Presence of antibodies may be associated with a higher incidence of injection site reactions and reports of low blood glucose. In clinical trials, these events were usually classified as mild and resolved while patients continued on treatment.

In a pediatric clinical trial, anti-liraglutide antibodies were detected in 14 (12%) of 117 SAXENDA-treated patients with a post-baseline assessment; 5 (4.3%) had persistent antibodies as defined by more than 2 antibody visits at least 16 weeks apart. Two patients (1.7%) remained positive throughout the follow-up period; 1 (0.9%) had antibodies cross reactive to native GLP-1. No patients had neutralizing antibodies.

Allergic Reactions

Urticaria was reported in 0.7% of SAXENDA-treated patients and 0.5% of placebo-treated patients. Anaphylactic reactions, asthma, bronchial hyperreactivity, bronchospasm, oropharyngeal swelling, facial swelling, angioedema, pharyngeal edema, type IV hypersensitivity reactions have been reported in patients treated with liraglutide in clinical trials. Cases of anaphylactic reactions with additional symptoms such as hypotension, palpitations, dyspnea, and edema have been reported with marketed use of liraglutide. Anaphylactic reactions may potentially be life-threatening.

Breast Cancer

In SAXENDA clinical trials in adults, breast cancer confirmed by adjudication was reported in 17 (0.7%) of 2379 SAXENDA-treated women compared with 3 (0.2%) of 1300 placebo-treated women, including invasive cancer (13 SAXENDA- and 2 placebo-treated women) and ductal carcinoma in situ (4 SAXENDA- and 1 placebo-treated woman). The majority of cancers were estrogen- and progesterone-receptor positive. There were too few cases to determine whether these cases were related to SAXENDA. In addition, there are insufficient data to determine whether SAXENDA has an effect on pre-existing breast neoplasia.

Papillary Thyroid Cancer

In SAXENDA clinical trials in adults, papillary thyroid carcinoma confirmed by adjudication was reported in 8 (0.2%) of 3291 SAXENDA-treated patients compared with no cases among 1843 placebo-treated patients. Four of these papillary thyroid carcinomas were less than 1 cm in greatest diameter and 4 were diagnosed in surgical pathology specimens after thyroidectomy prompted by findings identified prior to treatment.

Colorectal Neoplasms

In SAXENDA clinical trials in adults, benign colorectal neoplasms (mostly colon adenomas) confirmed by adjudication were reported in 20 (0.6%) of 3291 SAXENDA-treated patients compared with 7 (0.4%) of 1843 placebo-treated patients. Six positively adjudicated cases of malignant colorectal neoplasms were reported in 5 SAXENDA-treated patients (0.2%, mostly adenocarcinomas) and 1 in a placebo-treated patient (0.1%, neuroendocrine tumor of the rectum).

Cardiac Conduction Disorders

In SAXENDA clinical trials in adults, 11 (0.3%) of 3384 SAXENDA-treated patients compared with none of the 1941 placebo-treated patients had a cardiac conduction disorder, reported as first degree atrioventricular block, right bundle branch block, or left bundle branch block.

Hypotension

Adverse reactions related to hypotension (hypotension, orthostatic hypotension, circulatory collapse, and decreased blood pressure) were reported more frequently with SAXENDA (1.1%) compared with placebo (0.5%) in SAXENDA clinical trials in adults. Systolic blood pressure decreases to less than 80 mmHg were observed in 4 (0.1%) SAXENDA-treated patients compared with no placebo-treated patients. One of the SAXENDA-treated patients had hypotension associated with gastrointestinal adverse reactions and renal failure [see Warnings and Precautions (5.6)].

Laboratory Abnormalities

Liver Enzymes

Increases in alanine aminotransferase (ALT) greater than or equal to 10 times the upper limit of normal were observed in 5 (0.15%) SAXENDA-treated patients (two of whom had ALT greater than 20 and 40 times the upper limit of normal) compared with 1 (0.05%) placebo-treated patient during the SAXENDA clinical trials. Because clinical evaluation to exclude alternative causes of ALT and aspartate aminotransferase (AST) increases was not done in most cases, the relationship to SAXENDA is uncertain. Some increases in ALT and AST were associated with other confounding factors (such as gallstones).

Serum Calcitonin

Calcitonin, a biological marker of MTC, was measured throughout the clinical development program [see Warnings and Precautions (5.1)]. More patients treated with SAXENDA in the clinical trials were observed to have high calcitonin values during treatment, compared with placebo. The proportion of patients with calcitonin greater than or equal to 2 times the upper limit of normal at the end of the trial was 1.2% in SAXENDA-treated patients and 0.6% in placebo-treated patients. Calcitonin values greater than 20 ng/L at the end of the trial occurred in 0.5% of SAXENDA-treated patients and 0.2% of placebo-treated patients; among patients with pre-treatment serum calcitonin less than 20 ng/L, none had calcitonin elevations to greater than 50 ng/L at the end of the trial.

Serum Lipase and Amylase

Serum lipase and amylase were routinely measured in the SAXENDA clinical trials. Among SAXENDA-treated patients, 2.1% had a lipase value at anytime during treatment of greater than or equal to 3 times the upper limit of normal compared with 1.0% of placebo-treated patients. 0.1% of SAXENDA-treated patients had an amylase value at anytime in the trial of greater than or equal to 3 times the upper limit of normal versus 0.1% of placebo-treated patients. The clinical significance of elevations in lipase or amylase with SAXENDA is unknown in the absence of other signs and symptoms of pancreatitis [see Warnings and Precautions (5.2)].

6.2 Postmarketing Experience

The following adverse reactions have been reported during post-approval use of liraglutide, the active ingredient of SAXENDA. Because these reactions are reported voluntarily from a population of uncertain size, it is not always possible to reliably estimate their frequency or establish a causal relationship to drug exposure.

Gastrointestinal

Acute pancreatitis; hemorrhagic and necrotizing pancreatitis, sometimes resulting in death; ileus, intestinal obstruction, severe constipation including fecal impaction, nausea, vomiting and diarrhea leading to dehydration

Hepatobiliary

Hyperbilirubinemia, elevations of liver enzymes, cholestasis and hepatitis

Hypersensitivity

Rash, pruritus, angioedema and anaphylactic reactions

Neoplasms

Medullary thyroid carcinoma

Neurologic

Dysesthesia, headache

Pulmonary

Pulmonary aspiration has occurred in patients receiving GLP-1 receptor agonists undergoing elective surgeries or procedures requiring general anesthesia or deep sedation.

Renal

Acute kidney injury, sometimes requiring hemodialysis; increased serum creatinine

General Disorders and Administration Site Conditions

Allergic reactions: rash and pruritus

Immune System

Angioedema and anaphylactic reactions

Skin and Subcutaneous Tissue

Cutaneous amyloidosis, alopecia

7 DRUG INTERACTIONS

7.1 Oral Medications

SAXENDA causes a delay of gastric emptying, and thereby has the potential to impact the absorption of concomitantly administered oral medications. In clinical pharmacology trials, liraglutide did not affect the absorption of the tested orally administered medications to any clinically relevant degree. Nonetheless, monitor for potential consequences of delayed absorption of oral medications concomitantly administered with SAXENDA.

8 USE IN SPECIFIC POPULATIONS

8.1 Pregnancy

Risk Summary

Based on animal reproduction studies, there may be risks to the fetus from exposure to SAXENDA during pregnancy. SAXENDA should be used during pregnancy only if the potential benefit justifies the potential risk to the fetus. Additionally, weight loss offers no benefit to a pregnant patient and may cause fetal harm. When a pregnancy is recognized, advise the pregnant patient of the risk to a fetus, and discontinue SAXENDA (see Clinical Considerations).

Animal reproduction studies identified increased adverse embryofetal developmental outcomes from exposure during pregnancy. Liraglutide exposure was associated with early embryonic deaths and an imbalance in some fetal abnormalities in pregnant rats administered liraglutide during organogenesis at doses that approximate clinical exposures at the maximum recommended human dose (MRHD) of 3 mg/day. In pregnant rabbits administered liraglutide during organogenesis, decreased fetal weight and an increased incidence of major fetal abnormalities were seen at exposures below the human exposures at the MRHD (see Animal Data).

The estimated background risk of major birth defects and miscarriage for the indicated populations is unknown.

In the U.S. general population, the estimated background risk of major birth defects and miscarriage of clinically recognized pregnancies is 2 to 4% and 15 to 20%, respectively.

Clinical Considerations

Disease-associated maternal and/or embryofetal risk

Appropriate weight gain based on pre-pregnancy weight is currently recommended for all pregnant patients, including those who already have overweight or obesity, because of the obligatory weight gain that occurs in maternal tissues during pregnancy.

Animal Data

Liraglutide has been shown to be teratogenic in rats at or above 0.8-times systemic exposures in obese humans resulting from the maximum recommended human dose (MRHD) of 3 mg/day based on plasma area under the time-concentration curve (AUC) comparison. Liraglutide has been shown to cause reduced growth and increased total major abnormalities in rabbits at systemic exposures below exposure in obese humans at the MRHD based on plasma AUC comparison.

Female rats given subcutaneous doses of 0.1, 0.25 and 1 mg/kg/day liraglutide beginning 2 weeks before mating through gestation day 17 had estimated systemic exposures 0.8-, 3-, and 11-times the exposure in obese humans at the MRHD based on plasma AUC comparison. The number of early embryonic deaths in the 1 mg/kg/day group increased slightly. Fetal abnormalities and variations in kidneys and blood vessels, irregular ossification of the skull, and a more complete state of ossification occurred at all doses. Mottled liver and minimally kinked ribs occurred at the highest dose. The incidence of fetal malformations in liraglutide-treated groups exceeding concurrent and historical controls were misshapen oropharynx and/or narrowed opening into larynx at 0.1 mg/kg/day and umbilical hernia at 0.1 and 0.25 mg/kg/day.

Pregnant rabbits given subcutaneous doses of 0.01, 0.025 and 0.05 mg/kg/day liraglutide from gestation day 6 through day 18 inclusive, had estimated systemic exposures less than the exposure in obese humans at the MRHD of 3 mg/day at all doses, based on plasma AUC comparison. Liraglutide decreased fetal weight and dose-dependently increased the incidence of total major fetal abnormalities at all doses. The incidence of malformations exceeded concurrent and historical controls at 0.01 mg/kg/day (kidneys, scapula), greater than or equal to 0.01 mg/kg/day (eyes, forelimb), 0.025 mg/kg/day (brain, tail and sacral vertebrae, major blood vessels and heart, umbilicus), greater than or equal to 0.025 mg/kg/day (sternum) and at 0.05 mg/kg/day (parietal bones, major blood vessels). Irregular ossification and/or skeletal abnormalities occurred in the skull and jaw, vertebrae and ribs, sternum, pelvis, tail, and scapula; and dose-dependent minor skeletal variations were observed. Visceral abnormalities occurred in blood vessels, lung, liver, and esophagus. Bilobed or bifurcated gallbladder was seen in all treatment groups, but not in the control group.

In pregnant female rats given subcutaneous doses of 0.1, 0.25 and 1 mg/kg/day liraglutide from gestation day 6 through weaning or termination of nursing on lactation day 24, estimated systemic exposures were 0.8-, 3-, and 11-times exposure in obese humans at the MRHD of 3 mg/day, based on plasma AUC comparison. A slight delay in parturition was observed in the majority of treated rats. Group mean body weight of neonatal rats from liraglutide-treated dams was lower than neonatal rats from control group dams. Bloody scabs and agitated behavior occurred in male rats descended from dams treated with 1 mg/kg/day liraglutide. Group mean body weight from birth to postpartum day 14 trended lower in F2 generation rats descended from liraglutide-treated rats compared to F2 generation rats descended from controls, but differences did not reach statistical significance for any group.

8.2 Lactation

Risk Summary

There are no data on the presence of liraglutide in human milk, the effects on the breastfed infant, or effects on milk production. Liraglutide was present in the milk of lactating rats (see Data).

The developmental and health benefits of breastfeeding should be considered along with the mother’s clinical need for SAXENDA and any potential adverse effects on the breastfed infant from SAXENDA or from the underlying maternal condition.

Data

In lactating rats, liraglutide was present unchanged in milk at concentrations approximately 50% of maternal plasma concentrations.

8.4 Pediatric Use

The safety and effectiveness of SAXENDA as an adjunct to a reduced-calorie diet and increased physical activity for chronic weight management have been established in pediatric patients aged 12 years and older with body weight above 60 kg and an initial BMI corresponding to 30 kg/m^2 or greater for adults (obese) by international cut-offs. Use of SAXENDA for this indication is supported by a 56-week double-blind, placebo-controlled clinical trial in 251 pediatric patients aged 12 to 17 years, a pharmacokinetic study in pediatric patients, and studies in adults with obesity [see Clinical Pharmacology (12.3), Clinical Studies (14.1, 14.2)].

In the pediatric clinical trial, there was one death due to suicide in a SAXENDA-treated patient [see Warnings and Precautions (5.9)]; one SAXENDA-treated patient had an event of pancreatitis [see Warnings and Precautions (5.2)]; more episodes of hypoglycemia confirmed by self blood glucose monitoring occurred in SAXENDA-treated patients compared to placebo [see Warnings and Precautions (5.4), Adverse Reactions (6.1)]; and mean increases in resting heart rate of 3 to 7 bpm from baseline were observed with SAXENDA-treated patients [see Warnings and Precautions (5.5)].

The safety and effectiveness of SAXENDA have not been established in patients less than 12 years of age.

8.5 Geriatric Use

In the SAXENDA clinical trials, 232 (6.9%) of the SAXENDA-treated patients were 65 years of age and over, and 17 (0.5%) of the SAXENDA-treated patients were 75 years of age and over. No overall differences in safety or effectiveness were observed between these patients and younger patients, but greater sensitivity of some older individuals cannot be ruled out.

8.6 Renal Impairment

There is limited experience with SAXENDA in patients with mild, moderate, and severe renal impairment, including end‑stage renal disease.

8.7 Hepatic Impairment

There is limited experience in patients with mild, moderate, or severe hepatic impairment. Therefore, SAXENDA should be used with caution in this patient population [see Clinical Pharmacology (12.3)].

10 OVERDOSAGE

Overdoses have been reported in clinical trials and post-marketing use of liraglutide. Effects have included severe nausea, severe vomiting and severe hypoglycemia. In the event of overdosage, consider contacting the Poison Help line (1-800-222-1222) or a medical toxicologist for additional overdosage management recommendations. Initiate appropriate supportive treatment according to the patient’s clinical signs and symptoms.

11 DESCRIPTION

SAXENDA contains liraglutide, an analog of human GLP-1 and acts as a GLP-1 receptor agonist. The peptide precursor of liraglutide, produced by a process that includes expression of recombinant DNA in Saccharomyces cerevisiae, has been engineered to be 97% homologous to native human GLP-1 by substituting arginine for lysine at position 34. Liraglutide is made by attaching a C-16 fatty acid (palmitic acid) with a glutamic acid spacer on the remaining lysine residue at position 26 of the peptide precursor. The molecular formula of liraglutide is C172H265N43O51 and the molecular weight is 3751.2 Daltons. The structural formula (Figure 1) is:

Figure 1. Structural Formula of liraglutide

SAXENDA injection is a sterile, aqueous, clear, colorless or almost colorless solution for subcutaneous use. Each 1 mL of SAXENDA solution contains 6 mg of liraglutide and the following inactive ingredients: disodium phosphate dihydrate, 1.42 mg; propylene glycol, 14 mg; phenol, 5.5 mg; and water for injection. SAXENDA has a pH of approximately 8.15, hydrochloric acid or sodium hydroxide may be added to adjust pH. Each prefilled pen contains a 3 mL solution of SAXENDA equivalent to 18 mg liraglutide (free-base, anhydrous).

12 CLINICAL PHARMACOLOGY

12.1 Mechanism of Action

Liraglutide is an acylated human GLP-1 receptor agonist with 97% amino acid sequence homology to endogenous human GLP-1(7-37). Like endogenous GLP-1, liraglutide binds to and activates the GLP-1 receptor, a cell-surface receptor coupled to adenylyl cyclase activation through the stimulatory G-protein, Gs. Endogenous GLP-1 has a half-life of 1.5 to 2 minutes due to degradation by the ubiquitous endogenous enzymes, dipeptidyl peptidase 4 (DPP-4) and neutral endopeptidases (NEP). Unlike native GLP-1, liraglutide is stable against metabolic degradation by both peptidases and has a plasma half-life of 13 hours after subcutaneous administration. The pharmacokinetic profile of liraglutide, which makes it suitable for once-daily administration, is a result of self-association that delays absorption, plasma protein binding, and stability against metabolic degradation by DPP-4 and NEP.

GLP-1 is a physiological regulator of appetite and calorie intake, and the GLP-1 receptor is present in several areas of the brain involved in appetite regulation. In animal studies, peripheral administration of liraglutide resulted in the presence of liraglutide in specific brain regions regulating appetite, including the hypothalamus. Although liraglutide activated neurons in brain regions known to regulate appetite, specific brain regions mediating the effects of liraglutide on appetite were not identified in rats.

12.2 Pharmacodynamics

Liraglutide lowers body weight through decreased calorie intake. Liraglutide does not increase 24-hour energy expenditure.

As with other GLP-1 receptor agonists, liraglutide stimulates insulin secretion and reduces glucagon secretion in a glucose-dependent manner. These effects can lead to a reduction of blood glucose.

Gastric Emptying

Liraglutide delays gastric emptying.

Cardiac Electrophysiology (QTc) in healthy volunteers

The effect of liraglutide on cardiac repolarization was tested in a QTc study. Liraglutide at steady-state concentrations after daily doses up to 1.8 mg did not produce QTc prolongation. The maximum liraglutide plasma concentration (Cmax) in overweight and obese subjects treated with liraglutide 3 mg is similar to the Cmax observed in the liraglutide QTc study in healthy volunteers.

12.3 Pharmacokinetics

Absorption - Following subcutaneous administration, maximum concentrations of liraglutide are achieved at 11 hours post dosing. The average liraglutide steady state concentration (AUCτ/24) reached approximately 116 ng/mL in obese (BMI 30-40 kg/m^2) subjects following administration of SAXENDA. Liraglutide exposure increased proportionally in the dose range of 0.6 mg to 3 mg. The intra-subject coefficient of variation for liraglutide AUC was 11% following single dose administration. Liraglutide exposures were considered similar among three subcutaneous injection sites (upper arm, abdomen, and thigh). Absolute bioavailability of liraglutide following subcutaneous administration is approximately 55%.

Distribution - The mean apparent volume of distribution after subcutaneous administration of liraglutide 3 mg is 20 to 25L (for a person weighing approximately 100 kg). The mean volume of distribution after intravenous administration of liraglutide is 0.07 L/kg. Liraglutide is extensively bound to plasma protein (greater than 98%).

Metabolism - During the initial 24 hours following administration of a single [3H]-liraglutide dose to healthy subjects, the major component in plasma was intact liraglutide. Liraglutide is endogenously metabolized in a similar manner to large proteins without a specific organ as a major route of elimination.

Elimination - Following a [3H]-liraglutide dose, intact liraglutide was not detected in urine or feces. Only a minor part of the administered radioactivity was excreted as liraglutide-related metabolites in urine or feces (6% and 5%, respectively). The majority of urine and feces radioactivity was excreted during the first 6 to 8 days. The mean apparent clearance following subcutaneous administration of a single dose of liraglutide is approximately 0.9 to 1.4 L/h with an elimination half-life of approximately 13 hours, making liraglutide suitable for once daily administration.

Specific Populations

Elderly - Age had no effect on the pharmacokinetics of liraglutide based on a pharmacokinetic study in healthy elderly subjects (65 to 83 years) and population pharmacokinetic analyses of data from overweight and obese patients 18 to 82 years of age [see Use in Specific Populations (8.5)].

Gender - Based on the results of population pharmacokinetic analyses, females have 24% lower weight adjusted clearance of SAXENDA compared to males.

Race and Ethnicity - Race and ethnicity had no effect on the pharmacokinetics of liraglutide based on the results of population pharmacokinetic analyses that included overweight and obese patients of White, Black or African American, Asian and Hispanic/Non-Hispanic Ethnic groups.

Body Weight - Body weight significantly affects the pharmacokinetics of liraglutide based on results of population pharmacokinetic analyses conducted in patients with body weight range of 60 to 234 kg. The exposure of liraglutide decreases as baseline body weight increases.

Pediatric - A population pharmacokinetic analysis was conducted for SAXENDA using data from 134 pediatric patients (12 to 17 years of age) with obesity. The liraglutide exposure in the pediatric patients was similar to that in adults with obesity [see Use in Specific Populations (8.4)].

Renal Impairment - The single-dose pharmacokinetics of liraglutide were evaluated in patients with varying degrees of renal impairment. Patients with mild (estimated creatinine clearance 50-80 mL/min) to severe (estimated creatinine clearance less than 30 mL/min) renal impairment and patients with end-stage renal disease requiring dialysis were included in the trial. Compared to healthy subjects, liraglutide AUC in mild, moderate, and severe renal impairment and in end-stage renal disease was on average 35%, 19%, 29% and 30% lower, respectively [see Use in Specific Populations (8.6)].

Hepatic Impairment - The single-dose pharmacokinetics of liraglutide were evaluated in patients with varying degrees of hepatic impairment. Patients with mild (Child Pugh score 5 to 6) to severe (Child Pugh score greater than 9) hepatic impairment were included in the trial. Compared to healthy subjects, liraglutide AUC in subjects with mild, moderate and severe hepatic impairment was on average 11%, 14% and 42% lower, respectively [see Use in Specific Populations (8.7)].

Drug Interactions

In vitro assessment of drug-drug interactions

Liraglutide has low potential for pharmacokinetic drug-drug interactions related to cytochrome P450 (CYP) and plasma protein binding.

In vivo assessment of drug-drug interactions

The drug-drug interaction studies were performed at steady state with liraglutide 1.8 mg/day. The effect on rate of gastric emptying was equivalent between liraglutide 1.8 mg and 3 mg (acetaminophen AUC0-300min).

Administration of the interacting drugs was timed so that Cmax of liraglutide (8-12 h) would coincide with the absorption peak of the co-administered drugs.

Oral Contraceptives

A single dose of an oral contraceptive combination product containing 0.03 mg ethinylestradiol and 0.15 mg levonorgestrel was administered under fed conditions and 7 hours after the dose of liraglutide at steady state. Liraglutide lowered ethinylestradiol and levonorgestrel Cmax by 12% and 13%, respectively. There was no effect of liraglutide on the overall exposure (AUC) of ethinylestradiol. Liraglutide increased the levonorgestrel AUC0-∞ by 18%. Liraglutide delayed Tmax for both ethinylestradiol and levonorgestrel by 1.5 h.

Digoxin

A single dose of digoxin 1 mg was administered 7 hours after the dose of liraglutide at steady state. The concomitant administration with liraglutide resulted in a reduction of digoxin AUC by 16%; Cmax decreased by 31%. Digoxin median time to maximal concentration (Tmax) was delayed from 1 h to 1.5 h.

Lisinopril

A single dose of lisinopril 20 mg was administered 5 minutes after the dose of liraglutide at steady state. The coadministration with liraglutide resulted in a reduction of lisinopril AUC by 15%; Cmax decreased by 27%. Lisinopril median Tmax was delayed from 6 h to 8 h with liraglutide.

Atorvastatin

Liraglutide did not change the overall exposure (AUC) of atorvastatin following a single dose of atorvastatin 40 mg, administered 5 hours after the dose of liraglutide at steady state. Atorvastatin Cmax was decreased by 38% and median Tmax was delayed from 1 h to 3 h with liraglutide.

Acetaminophen

Liraglutide did not change the overall exposure (AUC) of acetaminophen following a single dose of acetaminophen 1000 mg, administered 8 hours after the dose of liraglutide at steady state. Acetaminophen Cmax was decreased by 31% and median Tmax was delayed up to 15 minutes.

Griseofulvin

Liraglutide did not change the overall exposure (AUC) of griseofulvin following co-administration of a single dose of griseofulvin 500 mg with liraglutide at steady state. Griseofulvin Cmax increased by 37% while median Tmax did not change.

Insulin Detemir

No pharmacokinetic interaction was observed between liraglutide and insulin detemir when separate subcutaneous injections of insulin detemir 0.5 Unit/kg (single-dose) and liraglutide 1.8 mg (steady state) were administered to patients with type 2 diabetes mellitus.

13 NONCLINICAL TOXICOLOGY

13.1 Carcinogenesis, Mutagenesis, Impairment of Fertility

A 104-week carcinogenicity study was conducted in male and female CD-1 mice at doses of 0.03, 0.2, 1, and 3 mg/kg/day liraglutide administered by bolus subcutaneous injection yielding systemic exposures 0.2-, 2-, 10- and 43-times the exposure in obese humans, respectively, at the maximum recommended human dose (MRHD) of 3 mg/day based on plasma AUC comparison. A dose-related increase in benign thyroid C-cell adenomas was seen in the 1 and the 3 mg/kg/day groups with incidences of 13% and 19% in males and 6% and 20% in females, respectively. C-cell adenomas did not occur in control groups or 0.03 and 0.2 mg/kg/day groups. Treatment-related malignant C-cell carcinomas occurred in 3% of females in the 3 mg/kg/day group. Thyroid C-cell tumors are rare findings during carcinogenicity testing in mice. A treatment-related increase in fibrosarcomas was seen on the dorsal skin and subcutis, the body surface used for drug injection, in males in the 3 mg/kg/day group. These fibrosarcomas were attributed to the high local concentration of drug near the injection site. The liraglutide concentration in the clinical formulation (6 mg/mL) is 10-times higher than the concentration in the formulation used to administer 3 mg/kg/day liraglutide to mice in the carcinogenicity study (0.6 mg/mL).

A 104-week carcinogenicity study was conducted in male and female Sprague Dawley rats at doses of 0.075, 0.25 and 0.75 mg/kg/day liraglutide administered by bolus subcutaneous injection with exposures 0.5-, 2- and 7-times the exposure in obese humans, respectively, resulting from the MRHD based on plasma AUC comparison. A treatment-related increase in benign thyroid C-cell adenomas was seen in males in 0.25 and 0.75 mg/kg/day liraglutide groups with incidences of 12%, 16%, 42%, and 46% and in all female liraglutide-treated groups with incidences of 10%, 27%, 33%, and 56% in 0 (control), 0.075, 0.25, and 0.75 mg/kg/day groups, respectively. A treatment-related increase in malignant thyroid C-cell carcinomas was observed in all male liraglutide-treated groups with incidences of 2%, 8%, 6%, and 14% and in females at 0.25 and 0.75 mg/kg/day with incidences of 0%, 0%, 4%, and 6% in 0 (control), 0.075, 0.25, and 0.75 mg/kg/day groups, respectively. Thyroid C-cell carcinomas are rare findings during carcinogenicity testing in rats.

Studies in mice demonstrated that liraglutide-induced C-cell proliferation was dependent on the GLP-1 receptor and that liraglutide did not cause activation of the REarranged during Transfection (RET) proto-oncogene in thyroid C-cells.

Human relevance of thyroid C-cell tumors in mice and rats is unknown and has not been determined by clinical studies or nonclinical studies [see Boxed Warning, Warnings and Precautions (5.1)].

Liraglutide was negative with and without metabolic activation in the Ames test for mutagenicity and in a human peripheral blood lymphocyte chromosome aberration test for clastogenicity. Liraglutide was negative in repeat-dose in vivo micronucleus tests in rats.

In rat fertility studies using subcutaneous doses of 0.1, 0.25 and 1 mg/kg/day liraglutide, males were treated for 4 weeks prior to and throughout mating and females were treated 2 weeks prior to and throughout mating until gestation day 17. No direct adverse effects on male fertility was observed at doses up to 1 mg/kg/day, a high dose yielding an estimated systemic exposure 11-times the exposure in obese humans at the MRHD, based on plasma AUC comparison. In female rats, an increase in early embryonic deaths occurred at 1 mg/kg/day. Reduced body weight gain and food consumption were observed in females at the 1 mg/kg/day dose.

14 CLINICAL STUDIES

14.1 Weight Management Trials in Adults with Overweight or Obesity

The safety and efficacy of SAXENDA for chronic weight management in conjunction with reduced caloric intake and increased physical activity were studied in three 56-week, randomized, double-blind, placebo-controlled trials. In all studies, SAXENDA was titrated to 3 mg daily during a 4-week period. All patients received instruction for a reduced-calorie diet (approximately 500 kcal/day deficit) and physical activity counseling (recommended increase in physical activity of minimum 150 mins/week) that began with the first dose of study medication or placebo and continued throughout the trial.

Study 1 enrolled 3731 patients with obesity (BMI greater than or equal to 30 kg/m^2) or with overweight (BMI 27-29.9 kg/m^2) and at least one weight-related comorbid condition such as treated or untreated dyslipidemia or hypertension; patients with type 2 diabetes mellitus were excluded. Patients were randomized in a 2:1 ratio to either SAXENDA or placebo. Patients were stratified based on the presence or absence of abnormal blood glucose measurements at randomization. All patients were treated for up to 56 weeks. Those patients with abnormal glucose measurements at randomization (2254 of the 3731 patients) were treated for a total of 160 weeks. At baseline, mean age was 45 years (range 18 to 78), 79% were female, 85% were White, 10% were Black or African American, and 11% were Hispanic/Latino Ethnicity. Mean baseline body weight was 106.3 kg and mean BMI was 38.3 kg/m^2.

Study 2 was a 56-week trial that enrolled 635 patients with type 2 diabetes and with either overweight or obesity (as defined above). Patients were to have an HbA1c of 7% to 10% and be treated with metformin, a sulfonylurea, or a glitazone as single agent or in any combination, or with a reduced-calorie diet and physical activity alone. Patients were randomized in a 2:1 ratio to receive either SAXENDA or placebo. The mean age was 55 years (range 18 to 82), 50% were female, 83% were White, 12% were Black or African American, and 10% were Hispanic/Latino Ethnicity. Mean baseline body weight was 105.9 kg and mean BMI was 37.1 kg/m^2.

Study 3 was a 56-week trial that enrolled 422 patients with obesity (BMI greater than or equal to 30 kg/m^2) or with overweight (BMI 27-29.9 kg/m^2) and at least one weight-related comorbid condition such as treated or untreated dyslipidemia or hypertension; patients with type 2 diabetes mellitus were excluded. All patients were first treated with a low-calorie diet (total energy intake 1200-1400 kcal/day) in a run-in period lasting up to 12 weeks. Patients who lost at least 5% of their screening body weight after 4 to 12 weeks during the run-in were then randomized, with equal allocation, to receive either SAXENDA or placebo for 56 weeks. The mean age was 46 years (range 18 to 73), 81% were female, 84% were White, 13% were Black or African American, and 7% were Hispanic/Latino Ethnicity. Mean baseline body weight was 99.6 kg and mean BMI was 35.6 kg/m^2.

The proportions of patients who discontinued study drug in the 56-week trials were 27% for the SAXENDA-treated group and 35% for the placebo-treated group, and in the 160-week trial the proportions of patients who discontinued were 47% and 55%, respectively. In the 56-week trials, approximately 10% of patients treated with SAXENDA and 4% of patients treated with placebo discontinued treatment due to an adverse reaction [see Adverse Reactions (6.1)]. The majority of patients who discontinued SAXENDA due to adverse reactions did so during the first few months of treatment. In the 160-week trial the proportions of patients who discontinued due to an adverse reaction was 13% and 6% for SAXENDA- and placebo-treated patients, respectively.

Effect of SAXENDA on Body Weight in 56-week Trials

For Study 1 and Study 2, the primary efficacy parameters were mean percent change in body weight and the percentages of patients achieving greater than or equal to 5% and 10% weight loss from baseline to week 56. For Study 3, the primary efficacy parameters were mean percent change in body weight from randomization to week 56, the percentage of patients not gaining more than 0.5% body weight from randomization (i.e., after run-in) to week 56, and the percentage of patients achieving greater than or equal to 5% weight loss from randomization to week 56. Because losing at least 5% of fasting body weight through lifestyle intervention during the 4- to 12-week run-in was a condition for their continued participation in the randomized treatment period, the results may not reflect those expected in the general population.

Table 4 presents the results for the changes in weight observed in Studies 1, 2, and 3. After 56 weeks, treatment with SAXENDA resulted in a statistically significant reduction in weight compared with placebo. Statistically significantly greater proportions of patients treated with SAXENDA achieved 5% and 10% weight loss than those treated with placebo. In Study 3, statistically significantly more patients randomized to SAXENDA than placebo had not gained more than 0.5% of body weight from randomization to week 56.

Table 4. Changes in Weight at Week 56 for Studies 1, 2, and 3

 | Study 1 (Obesity or overweight with comorbidity) |  | Study 2 (Type 2 diabetes with obesity or overweight) |  | Study 3 (Obesity or overweight with comorbidity following at least 5% weight loss with diet)
 | SAXENDA N=2487 | Placebo N=1244 | SAXENDA N=423 | Placebo N=212 | SAXENDA N=212 | Placebo N=210
Weight
Baseline mean (SD) (kg) | 106.2 (21.2) | 106.2 (21.7) | 105.7 (21.9) | 106.5 (21.3) | 100.4 (20.8) | 98.7 (21.2)
Percent change from baseline (LSMean) | -7.4 | -3 | -5.4 | -1.7 | -4.9 | 0.3
Difference from placebo (LSMean) (95% CI) | -4.5* (-5.2; -3.8) |  | -3.7* (-4.7; -2.7) |  | -5.2* (-6.8; -3.5)
% of Patients losing greater than or equal to 5% body weight | 62.3% | 34.4% | 49% | 16.4% | 44.2% | 21.7%
Difference from placebo (LSMean) (95% CI) | 27.9* (23.9; 31.9) |  | 32.6* (25.1; 40.1) |  | 22.6* (13.9; 31.3)
% of Patients losing greater than 10% body weight | 33.9% | 15.4% | 22.4% | 5.5% | 25.4% | 6.9%
Difference from placebo (LSMean) (95% CI) | 18.5* (15.2; 21.7) |  | 16.9* (11.7; 22.1) |  | 18.5* (11.7; 25.3)

SD = Standard Deviation; CI = Confidence Interval

* p < 0.0001 compared to placebo. Type 1 error was controlled across the three endpoints.

Includes all randomized subjects who had a baseline body weight measurement. All available body weight data during the 56 week treatment period are included in the analysis. In Studies 1 and 2 missing values for week 56 were handled using multiple imputations analysis. In Study 3 missing values for week 56 were handled using weighted regression analysis.

The cumulative frequency distributions of change in body weight from baseline to week 56 are shown in Figure 2 for Studies 1 and 2. One way to interpret this figure is to select a change in body weight of interest on the horizontal axis and note the corresponding proportions of patients (vertical axis) in each treatment group who achieved at least that degree of weight loss. For example, note that the vertical line arising from ‑10% in Study 1 intersects the SAXENDA and placebo curves at approximately 34% and 15%, respectively, which correspond to the values shown in Table 4.

Figure 2. Change in body weight (%) from baseline to week 56 (Study 1 on left and Study 2 on right)

The time courses of weight loss with SAXENDA and placebo from baseline through week 56 are depicted in Figure 3 and Figure 4.

Figure 3. Change from baseline (%) in body weight (Study 1 on left and Study 2 on right)

Figure 4. Change from baseline (%) in body weight during Study 3

Effect of SAXENDA on Body Weight in a 160-week Trial (Study 1, Subset of Patients with Abnormal Blood Glucose at Randomization)

The numbers and percentages of patients known to have lost greater than or equal to 5% body weight at week 56 and/or week 160 in Study 1 (patients with abnormal glucose at randomization only) are summarized in Table 5 for descriptive purposes.

Table 5. Changes in Weight at Week 56 and Week 160 for Study 1 (Subset of Patients with Abnormal Blood Glucose at Randomization)

 | SAXENDA N=1505 | Placebo N=749
Baseline mean body weight (SD) (kg) | 107.5 (21.6) | 107.9 (21.8)
Number (%) of patients known to lose greater than or equal to 5% body weight at 56 weeks | 817 (56%) | 182 (25%)
Number (%) of patients known to lose greater than or equal to 5% body weight at 160 weeks | 424 (28%) | 102 (14%)
Number (%) of patients known to lose greater than or equal to 5% body weight at both 56 weeks and 160 weeks | 391 (26%) | 74 (10%)
Number (%) of patients with weight assessment at 160 weeks | 747 (50%) | 322 (43%)

SD = Standard Deviation

Includes all randomized subjects who had a baseline body weight measurement. All available body weight data at 56 and 160 weeks are included in the analysis.

Effect of SAXENDA on Anthropometry and Cardiometabolic Parameters in 56-week Trials

Changes in waist circumference and cardiometabolic parameters with SAXENDA are shown in Table 6 for Study 1 (patients without diabetes mellitus) and Table 7 for Study 2 (patients with type 2 diabetes). Results from Study 3, which also enrolled patients without diabetes mellitus, were similar to Study 1.

Table 6. Mean Changes in Anthropometry and Cardiometabolic Parameters in Study 1 (Patients without Diabetes)

 | SAXENDA N=2487 |  | Placebo N=1244
 | Baseline | Change from Baseline (LSMean^1) | Baseline | Change from Baseline (LSMean^1) | SAXENDA minus Placebo (LSMean)
Waist Circumference (cm) | 115 | -8.2 | 114.5 | -4 | -4.2
Systolic Blood Pressure (mmHg) | 123 | -4.3 | 123.3 | -1.5 | -2.8
Diastolic Blood Pressure (mmHg) | 78.7 | -2.7 | 78.9 | -1.8 | -0.9
Heart Rate (bpm)^2 | 71.4 | 2.6 | 71.3 | 0.1 | 2.5
HbA1c (%) | 5.6 | -0.3 | 5.6 | -0.1 | -0.2
 | Baseline | % Change from Baseline (LSMean^1) | Baseline | % Change from Baseline (LSMean^1) | Relative Difference of SAXENDA to Placebo (LSMean)
Total Cholesterol (mg/dL)* | 193.8 | -3.2 | 194.4 | -0.9 | -2.3
LDL Cholesterol (mg/dL)* | 111.8 | -3.1 | 112.3 | -0.7 | -2.4
HDL Cholesterol (mg/dL)* | 51.4 | 2.3 | 50.9 | 0.5 | 1.9
Triglycerides (mg/dL)† | 125.7 | -13 | 128.3 | -4.1 | -7.1

Based on last observation carried forward method while on study drug
^1 Least squares mean adjusted for treatment, country, sex, pre-diabetes status at screening, baseline BMI stratum and an interaction between pre-diabetes status at screening and BMI stratum as fixed factors, and the baseline value as covariate.
^2 See Warnings and Precautions (5.5)
* Baseline value is the geometric mean
†Values are baseline median, median % change, and the Hodges-Lehmann estimate of the median treatment difference.
  Table 7. Mean Changes in Anthropometry and Cardiometabolic Parameters in Study 2 (Patients with Diabetes Mellitus)

 | SAXENDA N=423 |  | Placebo N=212
 | Baseline | Change from Baseline (LSMean^1) | Baseline | Change From Baseline (LSMean^1) | SAXENDA minus Placebo (LSMean)
Waist Circumference (cm) | 118.1 | -6 | 117.3 | -2.8 | -3.2
Systolic Blood Pressure (mmHg) | 128.9 | -3 | 129.2 | -0.4 | -2.6
Diastolic Blood Pressure (mmHg) | 79 | -1 | 79.3 | -0.6 | -0.4
Heart Rate (bpm)^2 | 74 | 2 | 74 | -1.5 | 3.4
HbA1c (%) | 7.9 | -1.3 | 7.9 | -0.4 | -0.9
 | Baseline | % Change from Baseline (LSMean^1) | Baseline | % Change From Baseline (LSMean^1) | Relative Difference of SAXENDA to Placebo (LSMean)
Total Cholesterol (mg/dL)* | 171 | -1.4 | 169.4 | 2.4 | -3.7
LDL Cholesterol (mg/dL)* | 86.4 | 0.9 | 85.2 | 3.3 | -2.3
HDL Cholesterol (mg/dL)* | 45.2 | 4.8 | 45.4 | 1.9 | 2.9
Triglycerides (mg/dL)† | 156.2 | -14.5 | 155.8 | -0.7 | -13.5

Based on last observation carried forward method while on study drug

^1 Least squares mean adjusted for treatment, country, sex, background treatment, baseline HbA1c stratum and an interaction between background treatment and HbA1c stratum as fixed factors, and the baseline value as covariate.

^2 See Warnings and Precautions (5.5)

* Baseline value is the geometric mean

† Values are baseline median, median % change, and the Hodges-Lehmann estimate of the median treatment difference.

14.2 Weight Management Trial in Pediatric Patients Ages 12 and Older with Obesity

SAXENDA was evaluated in a 56-week, double-blind, randomized, parallel group, placebo controlled multi-center trial in 251 pubertal pediatric patients aged 12 to 17 years, with BMI corresponding to 30 kg/m^2 or greater for adults by international cut-off points^1 and BMI of 95th percentile or greater for age and sex (NCT02918279). After a 12-week lifestyle run-in period, patients were randomized 1:1 to SAXENDA once-daily or placebo once-daily. The SAXENDA dose was titrated to 3 mg over a 4- to 8-week period based on tolerability as judged by the investigator. Escalation of the trial product was not allowed if the subject had a self-monitored plasma glucose (SMPG) <56 mg/dL or <70 mg/dL in the presence of symptoms of hypoglycemia during the week prior to or during the dose escalation visits. The proportion of patients who reached the 3 mg dose was 82.4%; for 8.8% of patients 2.4 mg was the maximum tolerated dose.

The mean age was 14.5 years: 40.6% of patients were male, 87.6% were White, 0.8% were Asian, 8% were Black or African American; 22.3% were of Hispanic or Latino ethnicity. The mean baseline body weight was 100.8 kg, and mean Body Mass Index (BMI) was 35.6 kg/m^2.

The proportions of patients who discontinued study drug were 19.2% for the SAXENDA-treated group and 20.6% for the placebo-treated group; 10.4% of patients treated with SAXENDA and no patients treated with placebo discontinued treatment due to an adverse reaction [see Adverse Reactions (6.1)].

The primary endpoint was change in BMI SDS. At baseline, mean BMI SDS was 3.14 in the SAXENDA group and 3.20 in the placebo group. At week 56, treatment with SAXENDA resulted in statistically significant reduction in BMI SDS from baseline compared to placebo. The observed mean change in BMI SDS from baseline to week 56 was -0.23 in the SAXENDA group and -0.00 in the placebo group. The estimated treatment difference in BMI SDS reduction from baseline between SAXENDA and placebo was -0.22 with a 95% confidence interval of -0.37, -0.08; p=0.0022.

The time course of change in BMI SDS with SAXENDA and placebo from baseline through week 56 are depicted in Figure 5.

Figure 5. Change from Baseline in BMI SDS

Changes in weight and BMI with SAXENDA are shown in Table 8. Changes in waist circumference and cardiometabolic parameters with SAXENDA are shown in Table 9.

Table 8. Changes in Weight and BMI at Week 56 for Study 4 (Pediatric Patients Ages 12 to Less than 18)

 | SAXENDA N=125 | Placebo N=126 | SAXENDA minus Placebo
Body Weight
Baseline mean Body Weight (kg) | 99.3 | 102.2
Mean Change from Baseline (%) | -2.65 | 2.37 | -5.01
BMI
Baseline mean BMI (kg/m^2) | 35.3 | 35.8
Mean Change from Baseline (%) | -4.29 | 0.35 | -4.64
Proportion of patients with greater than or equal to 5% reduction in baseline BMI at week 56 (%) | 43.3% | 18.7% | 24.6%
Proportion of patients with greater than or equal to 10% reduction in baseline BMI at week 56 (%) | 26.1% | 8.1% | 18%

Full Analysis Set. For body weight and BMI, baseline values are means, changes from baseline at week 56 are estimated means (least-squares) and treatment contrasts at week 56 are estimated treatment differences. Missing observations were imputed from the placebo arm based on a jump to reference multiple (x100) imputation approach.

Table 9. Mean Changes in Anthropometry and Cardiometabolic Parameters in Study 4 (Pediatric Patients Ages 12 to Less than 18)

 | SAXENDA N=125 |  | Placebo N=126
 | Baseline | Change from Baseline | Baseline | Change from Baseline | SAXENDA minus Placebo
Waist Circumference (cm) | 105 | -4.35 | 107 | -1.42 | -2.93
Systolic Blood Pressure (mmHg) | 116 | -1.21 | 117 | 0.84 | -2.05
Diastolic Blood Pressure (mmHg) | 72 | 0.77 | 73 | -0.46 | 1.24
Heart Rate (bpm)* | 75 | 1.87 | 78 | -0.14 | 2.01
HbA1c (%) | 5.3 | -0.1 | 5.3 | -0.03 | -0.06
 | Baseline | % Change from Baseline | Baseline | % Change from Baseline | Relative Difference of SAXENDA to Placebo
Total Cholesterol (mg/dL)** | 154.2 | 0.84 | 152.2 | -0.03 | 0.88
LDL Cholesterol (mg/dL)** | 85.5 | 1.74 | 82.5 | 3.01 | -1.27
HDL Cholesterol (mg/dL)** | 42.7 | 5.14 | 42.7 | 3.33 | 1.81
Triglycerides (mg/dL)** | 109.1 | -0.12 | 112.2 | -1.35 | 1.23
* See Warnings and Precautions (5.5)

Full Analysis Set. Baseline values are means, changes from baseline at week 56 are estimated means (least-squares) and treatment contrasts at week 56 are estimated treatment differences. Missing observations were imputed from the placebo arm based on a jump to reference multiple (x100) imputation approach.

** Baseline values are geometric means.

15 REFERENCES

1. Cole TJ, Bellizzi MC, Flegal KM, Dietz WH. Establishing a standard definition for child overweight and obesity worldwide: international survey. BMJ. 2000;320(7244):1240-3.

16 HOW SUPPLIED/STORAGE AND HANDLING

How Supplied

SAXENDA injection: 6 mg/mL clear, colorless solution in a 3 mL single-patient-use prefilled pen that delivers doses of 0.6 mg, 1.2 mg, 1.8 mg, 2.4 mg or 3 mg is available in the following package sizes:

3 x SAXENDA pen NDC 0169-2800-13

5 x SAXENDA pen NDC 0169-2800-15

Recommended Storage

Prior to first use, SAXENDA should be stored in a refrigerator between 36ºF to 46ºF (2ºC to 8ºC). Do not store in the freezer or directly adjacent to the refrigerator cooling element. Do not freeze SAXENDA and do not use SAXENDA if it has been frozen.

After initial use of the SAXENDA pen, the pen can be stored for 30 days at controlled room temperature 59°F to 86°F (15°C to 30°C) or in a refrigerator 36°F to 46°F (2°C to 8°C). Keep the pen cap on when not in use. Protect SAXENDA from excessive heat and sunlight. Always remove and safely discard the needle after each injection and store the SAXENDA pen without an injection needle attached. This will reduce the potential for contamination, infection, and leakage while also ensuring dosing accuracy.

17 PATIENT COUNSELING INFORMATION

Advise the patient to read the FDA-approved patient labeling (Medication Guide and Instructions for Use).

Instructions

Advise patients to take SAXENDA exactly as prescribed. Instruct patients to follow the dose escalation schedule and to not take more than the recommended dose.

Instruct adult patients to discontinue SAXENDA if they have not achieved 4% weight loss by 16 weeks of treatment. Instruct pediatric patients 12 years of age and older to discontinue SAXENDA if they have not achieved a BMI reduction of 1% from baseline after 12 weeks on the maintenance dose.

Risk of Thyroid C-cell Tumors

Inform patients that liraglutide causes benign and malignant thyroid C-cell tumors in mice and rats and that the human relevance of this finding has not been determined. Counsel patients to report symptoms of thyroid tumors (e.g., a lump in the neck, hoarseness, dysphagia or dyspnea) to their health care provider [see Boxed Warning, Warnings and Precautions (5.1)].

Acute Pancreatitis

Inform patients of the potential risk for acute pancreatitis and its symptoms: severe abdominal pain that may radiate to the back, and which may or may not be accompanied by nausea or vomiting. Instruct patients to discontinue SAXENDA promptly and contact their healthcare provider if pancreatitis is suspected [see Warnings and Precautions (5.2)].

Acute Gallbladder Disease

Inform patients of the risk of acute gallbladder disease. Advise patients that substantial or rapid weight loss can increase the risk of gallbladder disease, but that gallbladder disease may also occur in the absence of substantial or rapid weight loss. Instruct patients to contact their healthcare provider for appropriate clinical follow-up if gallbladder disease is suspected [see Warnings and Precautions (5.3)].

Hypoglycemia

Inform pediatric patients of the risk of hypoglycemia and educate all patients on the signs and symptoms of hypoglycemia. Inform adult patients with type 2 diabetes mellitus on an insulin secretagogue (e.g., sulfonylurea) or insulin that they may have an increased risk of hypoglycemia when using SAXENDA and to report signs and/or symptoms of hypoglycemia to their healthcare provider [see Warnings and Precautions (5.4)].

Heart Rate Increase

Inform patients to report symptoms of sustained periods of heart pounding or racing while at rest to their healthcare provider. Discontinue SAXENDA in patients who experience a sustained increase in resting heart rate [see Warnings and Precautions (5.5)].

Acute Kidney Injury Due to Volume Depletion

Inform patients of the potential risk of acute kidney injury due to dehydration associated with gastrointestinal

adverse reactions. Advise patients to take precautions to avoid fluid depletion. Inform patients of the signs and symptoms of acute kidney injury and instruct them to promptly report any of these signs or symptoms or

persistent (or extended) nausea, vomiting, and diarrhea to their healthcare provider [see Warnings and Precautions (5.6)].

Severe Gastrointestinal Adverse Reactions

Inform patients of the potential risk of severe gastrointestinal adverse reactions. Instruct patients to contact their healthcare provider if they have severe or persistent gastrointestinal symptoms [see Warnings and Precautions

(5.7)].

Hypersensitivity Reactions

Inform patients that serious hypersensitivity reactions have been reported during postmarketing use of SAXENDA. Advise patients on the symptoms of hypersensitivity reactions and instruct them to stop taking SAXENDA and seek medical advice promptly if such symptoms occur [see Warnings and Precautions (5.8)].

Suicidal Behavior and Ideation

Advise patients to report emergence or worsening of depression, suicidal thoughts or behavior, and/or any unusual changes in mood or behavior. Inform patients that if they experience suicidal thoughts or behaviors, they should stop taking SAXENDA [see Warnings and Precautions (5.9)].

Pulmonary Aspiration During General Anesthesia or Deep Sedation

Inform patients that SAXENDA may cause their stomach to empty more slowly which may lead to complications with anesthesia or deep sedation during planned surgeries or procedures. Instruct patients to inform healthcare providers prior to any planned surgeries or procedures if they are taking SAXENDA [see Warnings and Precautions (5.10)].

Never Share a SAXENDA Pen Between Patients

Inform patients that they should never share a SAXENDA pen with another person, even if the needle is changed. Sharing of the pen between patients may pose a risk of transmission of infection.

Marketed by: Novo Nordisk Inc., Plainsboro, NJ 08536

SAXENDA® and VICTOZA® are registered trademarks of Novo Nordisk A/S.

PATENT Information: http://novonordisk-us.com/products/product-patents.html

© 2025 Novo Nordisk

For information about SAXENDA contact:
Novo Nordisk Inc.
800 Scudders Mill Road
Plainsboro, NJ 08536

1-844-363-4448

Medication Guide

SAXENDA (sax-end-ah)

(liraglutide) injection, for subcutaneous use

What is the most important information I should know about SAXENDA?

Serious side effects may happen in people who take SAXENDA, including:

- Possible thyroid tumors, including cancer. Tell your healthcare provider if you get a lump or swelling in your neck, hoarseness, trouble swallowing, or shortness of breath. These may be symptoms of thyroid cancer. In studies with rats and mice, SAXENDA and medicines that work like SAXENDA caused thyroid tumors, including thyroid cancer. It is not known if SAXENDA will cause thyroid tumors or a type of thyroid cancer called medullary thyroid carcinoma (MTC) in people.
- Do not use SAXENDA if you or any of your family have ever had a type of thyroid cancer called medullary thyroid carcinoma (MTC), or if you have an endocrine system condition called Multiple Endocrine Neoplasia syndrome type 2 (MEN 2).

What is SAXENDA?

SAXENDA is an injectable prescription medicine used for adults with obesity or overweight (excess weight) who also have weight related medical problems, and children aged 12 to 17 years with a body weight above 132 pounds (60 kg) and obesity to help them lose weight and keep the weight off.

- SAXENDA should be used with a reduced calorie diet and increased physical activity.
- SAXENDA is not recommended for people who also take liraglutide or other medicines called glucagon-like peptide-1 (GLP-1) receptor agonists.
- It is not known if SAXENDA is safe and effective in children under 12 years of age.
- It is not known if SAXENDA is safe and effective in children aged 12 to 17 years with type 2 diabetes.

Who should not use SAXENDA?

Do not use SAXENDA if:

- you or any of your family have ever had a type of thyroid cancer called medullary thyroid carcinoma (MTC) or if you have an endocrine system condition called Multiple Endocrine Neoplasia syndrome type 2 (MEN 2).
- you have had a serious allergic reaction to liraglutide or any of the ingredients in SAXENDA. See the end of this Medication Guide for a complete list of ingredients in SAXENDA. See “What are the possible side effects of SAXENDA?” for symptoms of a serious allergic reaction.

Before taking SAXENDA, tell your healthcare provider about all of your medical conditions, including if you:

- have or have had problems with your pancreas.
- have severe problems with your stomach, such as slowed emptying of your stomach (gastroparesis) or problems with digesting food.
- are scheduled to have surgery or other procedures that use anesthesia or deep sleepiness (deep sedation).
- have or have had depression or suicidal thoughts, or mental health issues.
- are breastfeeding or plan to breastfeed. It is not known if SAXENDA passes into your breast milk. You and your healthcare provider should decide if you will use SAXENDA or breastfeed.

Tell your healthcare provider about all the medicines you take including prescription, over-the-counter medicines, vitamins, and herbal supplements. SAXENDA may affect the way some medicines work and some other medicines may affect the way SAXENDA works.

Tell your healthcare provider if you take diabetes medicines, especially insulin and sulfonylurea medicines. Talk with your healthcare provider if you are not sure if you take any of these medicines.

Know the medicines you take. Keep a list of them to show your healthcare provider and pharmacist when you get a new medicine.

How should I use SAXENDA?

- Read the Instructions for Use that comes with SAXENDA.
- Use SAXENDA exactly as your healthcare provider tells you to.
- Your healthcare provider should show you how to use SAXENDA before you use it for the first time.
- Use SAXENDA with a reduced-calorie diet and increased physical activity.
- SAXENDA is injected under the skin (subcutaneously) in your stomach area (abdomen), upper leg (thigh), or upper arm. Do not inject into a muscle (intramuscularly) or vein (intravenously).
- SAXENDA is injected 1 time each day, at any time during the day.
- Start SAXENDA with 0.6 mg per day in your first week. In your second week, increase your daily dose to 1.2 mg. In the third week, increase your daily dose to 1.8 mg. In the fourth week, increase your daily dose to 2.4 mg and in the fifth week onwards, increase your daily dose to the full dose of 3 mg. After that, do not change your dose unless your healthcare provider tells you to. Children may reduce their dose to 2.4 mg daily if the maximum dose is not tolerated.
- If you miss your daily dose of SAXENDA, just take your next daily dose as usual on the following day. Do not take an extra dose of SAXENDA or increase your dose on the following day to make up for your missed dose. If you miss your dose of SAXENDA for 3 days or more, call your healthcare provider to talk about how to restart your treatment.
- SAXENDA may be taken with or without food.
- Change (rotate) your injection site with each injection. Do not use the same site for each injection.
- Do not share your SAXENDA pen with other people, even if the needle has been changed. You may give other people a serious infection or get a serious infection from them.
- If you take too much SAXENDA, call your healthcare provider or Poison Help line at 1-800-222-1222 or go to the nearest hospital emergency room right away.
- Throw away the used SAXENDA pen after 30 days.

What are the possible side effects of SAXENDA?

SAXENDA may cause serious side effects, including:

- See “What is the most important information I should know about SAXENDA?”
- inflammation of the pancreas (pancreatitis). Stop using SAXENDA and call your healthcare provider right away if you have severe pain in your stomach area (abdomen) that will not go away, with or without vomiting. You may feel the pain from your stomach area (abdomen) to your back.
- increased risk of low blood sugar (hypoglycemia) in adults with type 2 diabetes, especially those who also take medicines to treat type 2 diabetes mellitus such as an insulin or a sulfonylureas and in children who are 12 years of age and older without type 2 diabetes mellitus. Low blood sugar in patients with adults with type 2 diabetes and in children without type 2 diabetes mellitus who receive SAXENDA can be both a serious and common side effect. Talk to your healthcare provider about how to recognize and treat low blood sugar. You should check your blood sugar before you start taking SAXENDA and while you take SAXENDA.

Signs and symptoms of low blood sugar may include:

  - dizziness or light-headedness
- sweating
- confusion or drowsiness
- headache

- blurred vision
- slurred speech
- shakiness
- fast heartbeat

- anxiety, irritability, or mood changes
- hunger
- weakness
- feeling jittery

Talk to your healthcare provider about how to recognize and treat low blood sugar. You should check your blood sugar before you start taking SAXENDA and while you take SAXENDA.
2. increased heart rate. SAXENDA can increase your heart rate while you are at rest. Your healthcare provider should check your heart rate while you take SAXENDA. Tell your healthcare provider if you feel your heart racing or pounding in your chest and it lasts for several minutes.
3. dehydration leading to kidney problems. Diarrhea, nausea, and vomiting may cause a loss of fluids (dehydration) which may cause kidney problems. It is important for you to drink fluids to help reduce your chance of dehydration. Tell your healthcare provider right away if you have nausea, vomiting, or diarrhea that does not go away.
4. severe stomach problems. Stomach problems, sometimes severe, have been reported in people who use SAXENDA. Tell your healthcare provider if you have stomach problems that are severe or will not go away.
5. serious allergic reactions. Stop using SAXENDA, and get medical help right away if you have any symptoms of a serious allergic reaction including:

- swelling of your face, lips, tongue, or throat
- problems breathing or swallowing
  - severe rash or itching

- fainting or feeling dizzy
- very rapid heartbeat

- gallbladder problems. SAXENDA may cause gallbladder problems including gallstones. Some gallbladder problems need surgery. Call your healthcare provider if you have any of the following symptoms:

- pain in your upper stomach (abdomen)
- fever

- yellowing of your skin or eyes (jaundice)
- clay-colored stools

- depression or thoughts of suicide. You should pay attention to any mental changes, especially sudden changes, in your mood, behaviors, thoughts, or feelings. Call your healthcare provider right away if you have any mental changes that are new, worse, or worry you.
- food or liquid getting into the lungs during surgery or other procedures that use anesthesia or deep sleepiness (deep sedation). SAXENDA may increase the chance of food getting into your lungs during surgery or other procedures. Tell all your healthcare providers that you are taking SAXENDA before you are scheduled to have surgery or other procedures.
The most common side effects of SAXENDA in adults include:

- nausea
- diarrhea
- constipation
- vomiting

- injection site reaction
- low blood sugar (hypoglycemia)
- headache
- upset stomach (dyspepsia)

- tiredness (fatigue)
- dizziness
- stomach pain

- change in enzyme (lipase) levels in your blood

Additional common side effects in children are fever and gastroenteritis

Talk to your healthcare provider if you have any side effect that bothers you or that does not go away.
These are not all the possible side effects of SAXENDA. Call your doctor for medical advice about side effects. You may report side effects to FDA at 1-800-FDA-1088.

Keep your SAXENDA pen, pen needles, and all medicines out of the reach of children.

General information about the safe and effective use of SAXENDA.

Medicines are sometimes prescribed for purposes other than those listed in a Medication Guide. Do not use SAXENDA for a condition for which it was not prescribed. Do not give SAXENDA to other people, even if they have the same symptoms that you have. It may harm them.

You can ask your pharmacist or healthcare provider for information about SAXENDA that is written for health professionals.

What are the ingredients in SAXENDA?

Active ingredient: liraglutide

Inactive ingredients: disodium phosphate dihydrate, propylene glycol, phenol and water for injection. Hydrochloric acid or sodium hydroxide may be added to adjust the pH.

Manufactured by: Novo Nordisk A/S, DK-2880 Bagsvaerd, Denmark.

For information about SAXENDA go to www.SAXENDA.com or contact: Novo Nordisk Inc., 800 Scudders Mill Road, Plainsboro, NJ 08536 1-844-363-4448

SAXENDA®, VICTOZA®, and NovoFine® are registered trademarks of Novo Nordisk A/S.

PATENT Information: http://novonordisk-us.com/products/product-patents.html

© 2025 Novo Nordisk

This Medication Guide has been approved by the U.S. Food and Drug Administration. Revised: 05/2025

Instructions for Use

- Read these instructions carefully before using your Saxenda® pen.
- Do not use your pen without proper training from your healthcare provider. Make sure that you know how to give yourself an injection with the pen before you start your treatment.
If you are blind or have poor eyesight and cannot read the dose counter on the pen, do not use this pen
without help. Get help from a person with good eyesight who is trained to use the Saxenda pen.
- You can refresh your training at any time by watching the online training video at www.saxenda.com.
- Start by checking your pen to make sure that it contains Saxenda, then look at the pictures below to get to know the different parts of your pen and needle.
Your pen is a prefilled, dial-a-dose, single-patient-use pen. It contains 18 mg of liraglutide, and you can select doses of 0.6 mg, 1.2 mg, 1.8 mg, 2.4 mg and 3 mg. Your pen is made to be used with NovoFine® or NovoTwist® disposable needles up to a length of 8 mm. Pen needles are not included with your Saxenda pen.

Step 1. Prepare your pen with a new needle

- Wash your hands with soap and water.
- Check the name and colored label of your pen, to make sure that it contains Saxenda. This is especially important if you take more than 1 type of medicine.
- Pull off the pen cap.

- Check that Saxenda in your pen is clear and colorless.
  Look through the pen window. If Saxenda looks cloudy, do not use the pen.

- Take a new needle, and tear off the paper tab.

- Push the needle straight onto the pen. Turn until it is on tight.

- Pull off the outer needle cap. Do not throw it away.

- Pull off the inner needle cap and throw it away.
  A drop of Saxenda may appear at the needle tip. This is normal, but you must still check the Saxenda flow, if you use a new pen for the first time.

Always use a new needle for each injection.

This will prevent contamination, infection, leakage of Saxenda,

and blocked needles leading to the wrong dose.
Never use a bent or damaged needle.

Do not attach a new needle to your pen until you are ready to

take your injection.

Step 2. Check the Saxenda flow with each new pen.

- Check the Saxenda flow before your first injection with each new pen.
  If your Saxenda pen is already in use, go to Step 3 “Select your dose”.
- Turn the dose selector until the dose counter shows the flow check symbol ().

- Hold the pen with the needle pointing up.
  Press and hold in the dose button until the dose counter shows 0. The 0 must line up with the dose pointer.
  A drop of Saxenda will appear at the needle tip.
- If no drop appears, repeat Step 2 above as shown in Figures G and H up to 6 times. If there is still no drop, change the needle and repeat Step 2 as shown in Figures G and H 1 more time.
  Do not use the pen if a drop of Saxenda still does not appear. Contact Novo Nordisk at 1-844-363-4448.

Always make sure that a drop appears at the needle tip before you use a new pen for the first time. This makes sure that Saxenda flows.
If no drop appears, you will not inject any Saxenda, even though the dose counter may move. This may mean that there is a blocked or damaged needle.

A small drop may remain at the needle tip, but it will not be injected.
Only check the Saxenda flow before your first injection with each new pen.

Step 3. Select your dose

- Turn the dose selector until the dose counter shows your dose (0.6 mg, 1.2 mg, 1.8 mg, 2.4 mg or 3 mg).
  Make sure you know the dose of Saxenda you should use.
If you select the wrong dose, you can turn the dose selector forward or backwards to the correct dose.

Always use the dose counter and the dose pointer to see how

many mg you select.

You will hear a “click” every time you turn the dose selector. Do

not set the dose by counting the number of clicks you hear.
Do not use the pen scale to set the dose. It does not show exactly

how much Saxenda is left in your pen.
Only doses of 0.6 mg, 1.2 mg, 1.8 mg, 2.4 mg or 3 mg can be

selected with the dose selector. The selected dose must line up

exactly with the dose pointer to make sure that you get a correct

dose.

The dose selector changes the dose. Only the dose counter and dose

pointer will show how many mg you select for each dose.

You can select up to 3 mg each dose. When your pen contains less

than 3 mg the dose counter stops before 3 mg is shown.
The dose selector clicks differently when turned forward,

backwards or past the number of mg left. Do not count the pen

clicks.

How much Saxenda is left?

- The pen scale shows you about how much Saxenda is left in your pen.

- To see how much Saxenda is left, use the dose counter:
  Turn the dose selector until the dose counter stops.
  If it shows 3, at least 3 mg are left in your pen. If the dose counter stops before 3 mg, there is not enough Saxenda left for a full dose of 3 mg.

If you need more Saxenda than what is left in your pen
Only if trained or told by your healthcare provider, you may split your dose between your current pen and a new pen. Use a calculator to plan the doses as instructed by your healthcare provider.

Be very careful to calculate correctly.
If you are not sure how to split your dose using 2 pens, then select and inject the dose you need with a new pen.

Step 4. Inject your dose

- Insert the needle into your skin as your healthcare provider has shown you.
- Make sure you can see the dose counter. Do not cover it with your fingers. This could stop the injection.

- Press and hold down the dose button until the dose counter shows 0. The 0 must line up with the dose pointer. You may then hear or feel a click.

- Keep the needle in your skin after the dose counter has returned to 0 and count slowly to 6.
- If the needle is removed earlier, you may see a stream of Saxenda coming from the needle tip. If this happens, the full dose will not be delivered.

- Remove the needle from your skin.
  If blood appears at the injection site, press lightly. Do not rub the area.

Always watch the dose counter to know how many mg you

inject. Hold the dose button down until the dose counter shows 0.

How to identify a blocked or damaged needle?

  - If 0 does not appear in the dose counter after continuously pressing the dose button, you may have used a blocked or damaged needle.
  - If this happens you have not received any Saxenda even though the dose counter has moved from the original dose that you have set.
How to handle a blocked needle?
Change the needle as described in Step 5, and repeat all steps
starting with Step 1: “Prepare your pen with a new needle”.
Make sure you select the full dose you need.
Never touch the dose counter when you inject. This can stop the
injection.

You may see a drop of Saxenda at the needle tip after injecting. This

is normal and does not affect your dose.

Step 5. After your injection

- Carefully remove the needle from the pen. Do not put the needle caps back on the needle, to avoid needle sticks.

- Place the needle in a sharps container right away to reduce the risk of needle sticks.

- Put the pen cap on your pen after each use to protect Saxenda from light.

If you do not have a sharps container, follow a 1-handed needle

recapping method. Carefully slip the needle into the outer needle

cap. Dispose of the needle in a sharps container as soon as possible.

Never try to put the inner needle cap back on the needle. You

may stick yourself with the needle.
Always remove the needle from your pen.
This prevents contamination, infection, leakage of Saxenda, and

blocked needles leading to the wrong dose. If the needle is

blocked, you will not inject any Saxenda.

Always dispose of the needle after each injection.

- Do not throw away in the household trash. Put the needle and any empty Saxenda pen or any pen used for 30 days still containing Saxenda in a FDA-cleared sharps disposal container right away after use.
- If you do not have a FDA-cleared sharps disposal container, you may use a household container that is:
  - made of a heavy-duty plastic
  - can be closed with a tight-fitting, puncture-resistant lid, without sharps being able to come out upright and stable during use
  - leak-resistant
  - properly labeled to warn of hazardous waste inside the container
- When your sharps disposal container is almost full, you will need to follow your community guidelines for the right way to dispose of your sharps disposal container. There may be state or local laws about how you should throw away used needles and syringes. For more information about the safe sharps disposal, and for specific information about sharps disposal in the state that you live in, go to the FDA’s website at: http://www.fda.gov/safesharpsdisposal
- Do not dispose of your used sharps disposal container in your household trash unless your community guidelines permit this. Do not recycle your used sharps disposal container.
- Safely dispose of Saxenda that is out of date or no longer needed.

Important

- Caregivers must be very careful when handling used needles to prevent needle sticks and cross infection.
- Never use a syringe to withdraw Saxenda from your pen.
- Always carry an extra pen and new needles with you, in case of loss or damage.
- Always keep your pen and needles out of reach of others, especially children.
- Do not share your Saxenda pen or needles with anyone else. You may give an infection to them or get an infection from them.
- Always keep your pen with you. Do not leave it in a car or other place where it can get too hot or too cold.

Caring for your pen

- Do not drop your pen or knock it against hard surfaces. If you drop it or suspect a problem, attach a new needle and check the Saxenda flow before you inject.
- Do not try to repair your pen or pull it apart.
- Do not expose your pen to dust, dirt or liquid.
- Do not wash, soak, or lubricate your pen. If necessary, clean it with mild detergent on a moistened cloth.

How should I store my Saxenda pen?

- Store your new, unused Saxenda pens in the refrigerator at 36°F to 46°F (2°C to 8°C).
- Store your pen in use for 30 days at 59ºF to 86ºF (15ºC to 30ºC) or in a refrigerator at 36°F to 46°F (2°C to 8°C).
- The Saxenda pen you are using should be thrown away after 30 days, even if it still has Saxenda left in it.
- Do not freeze Saxenda. Do not use Saxenda if it has been frozen.
- Unused Saxenda pens may be used until the expiration date printed on the label, if kept in the refrigerator.
- Keep Saxenda away from heat and out of the light.

This Medication Guide and Instructions for Use have been approved by the U.S. Food and Drug Administration.

December 2020

PRINCIPAL DISPLAY PANEL

NDC 0169-2800-15

List 280015

Saxenda ®

(liraglutide) injection

18 mg/3 mL (6 mg/mL)

5×3 mL Prefilled Pens

For subcutaneous use only

Rx Only

Single Patient Use Only

Discard pen 30 days after first use

Recommended for use with NovoFine® or NovoTwist® disposable needles.

REFRIGERATE – DO NOT FREEZE

Protect from light.

Dispense the enclosed Medication Guide to each patient